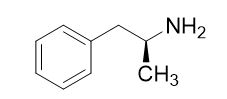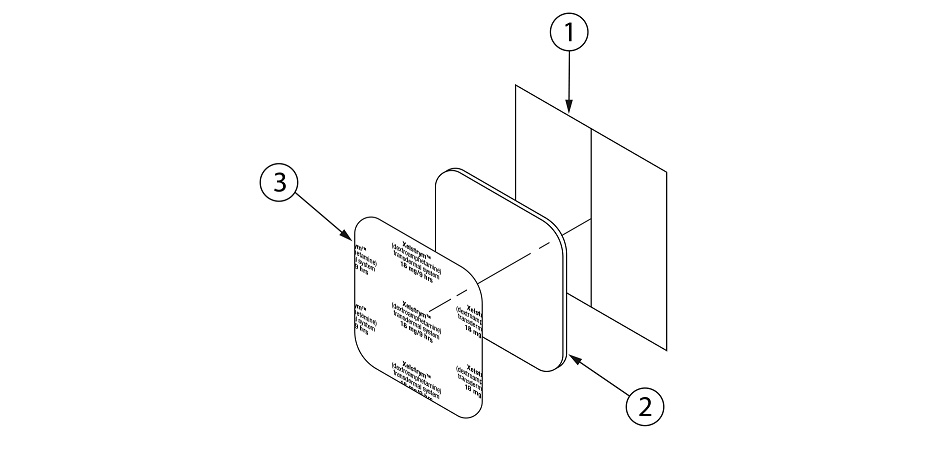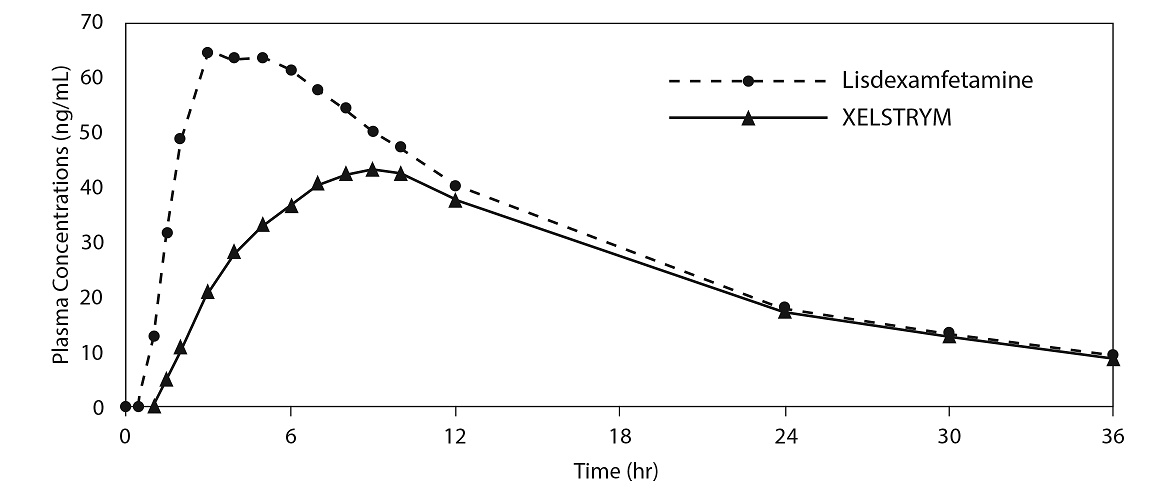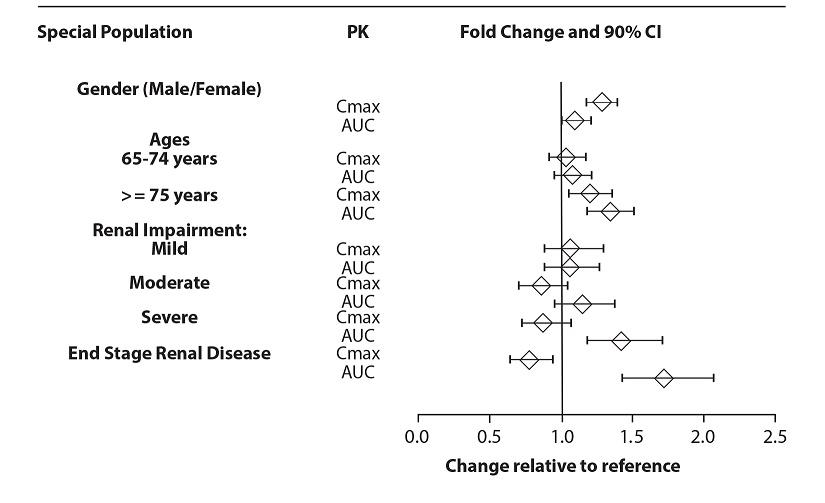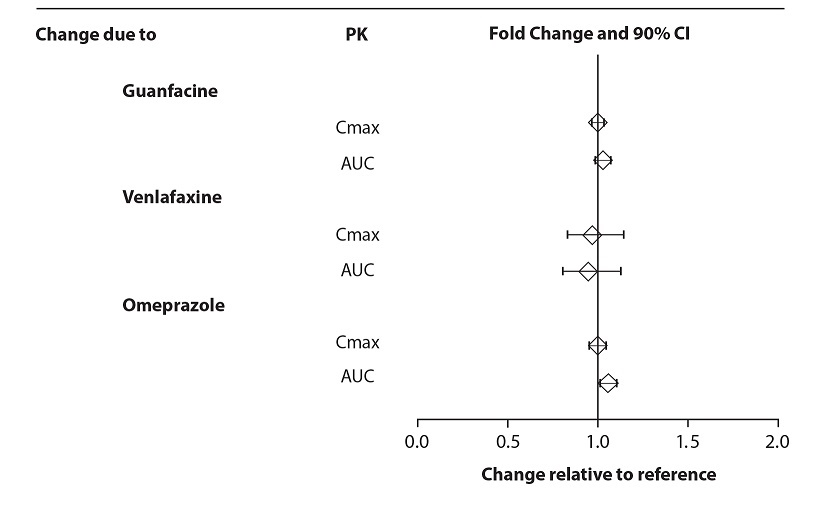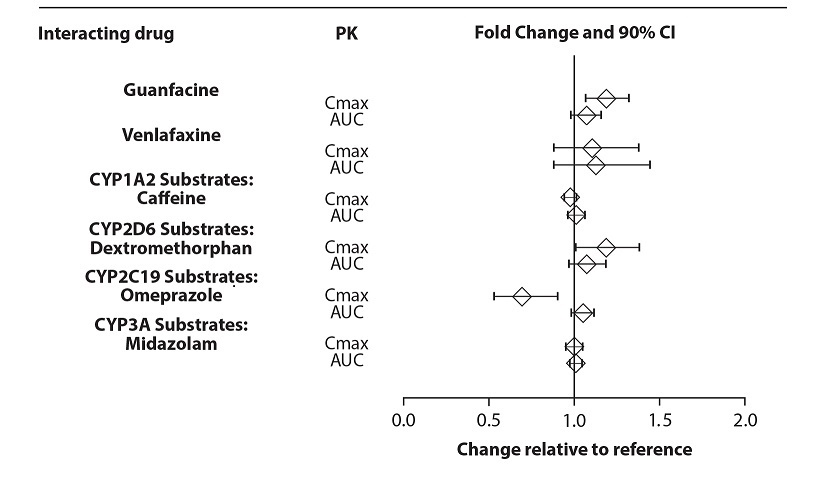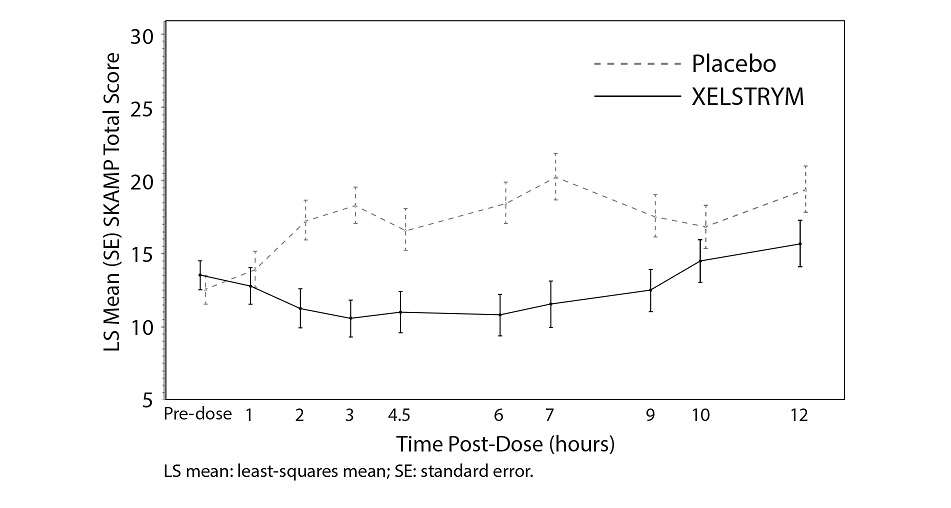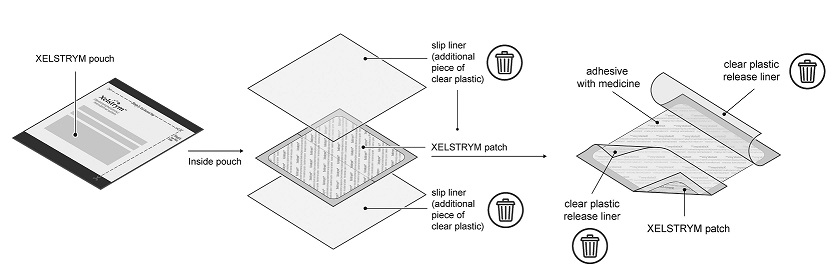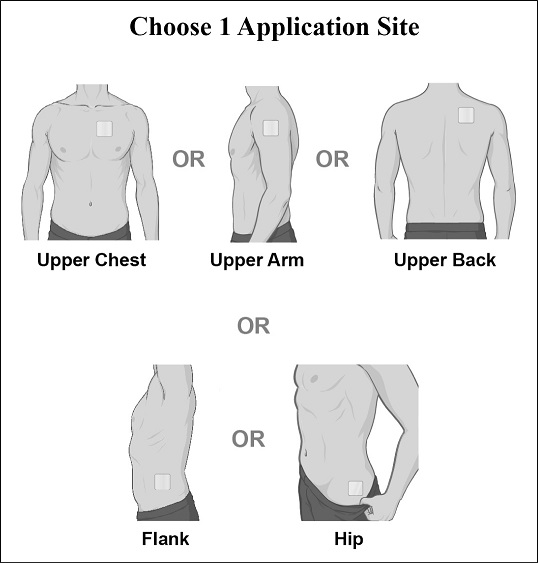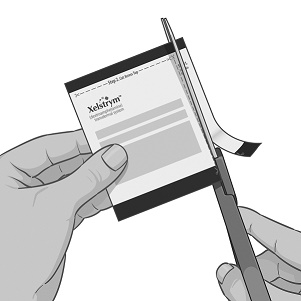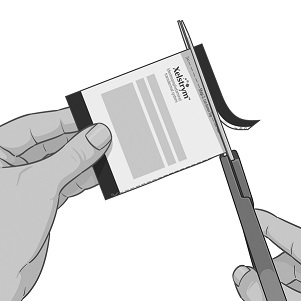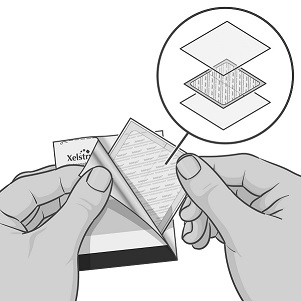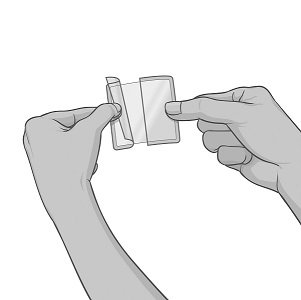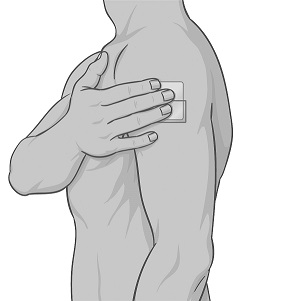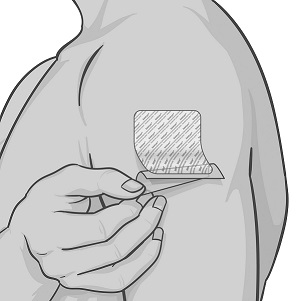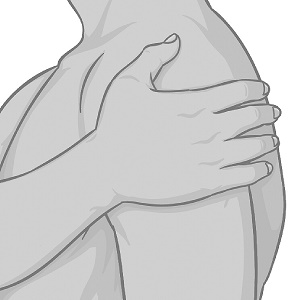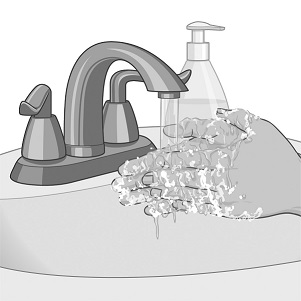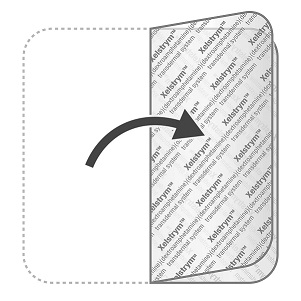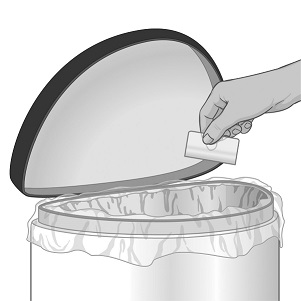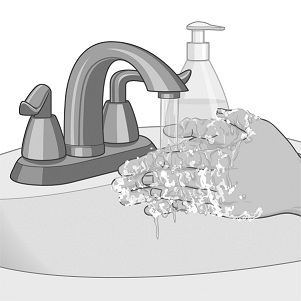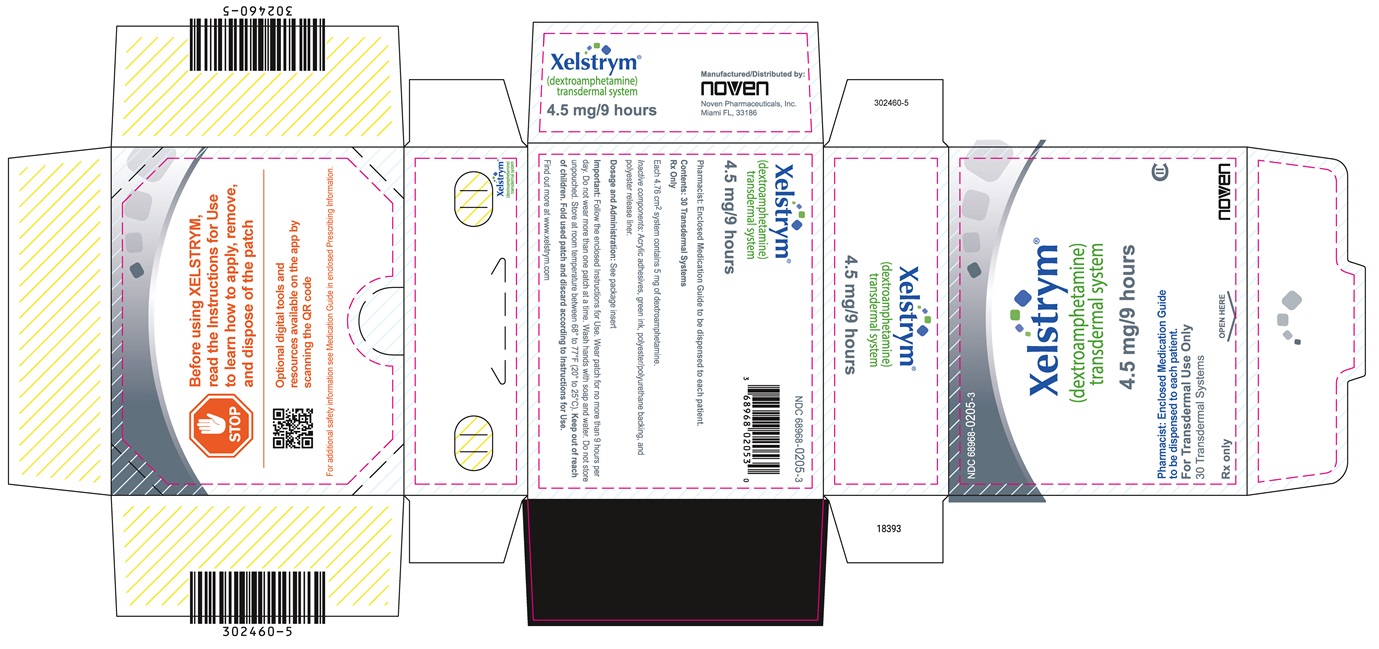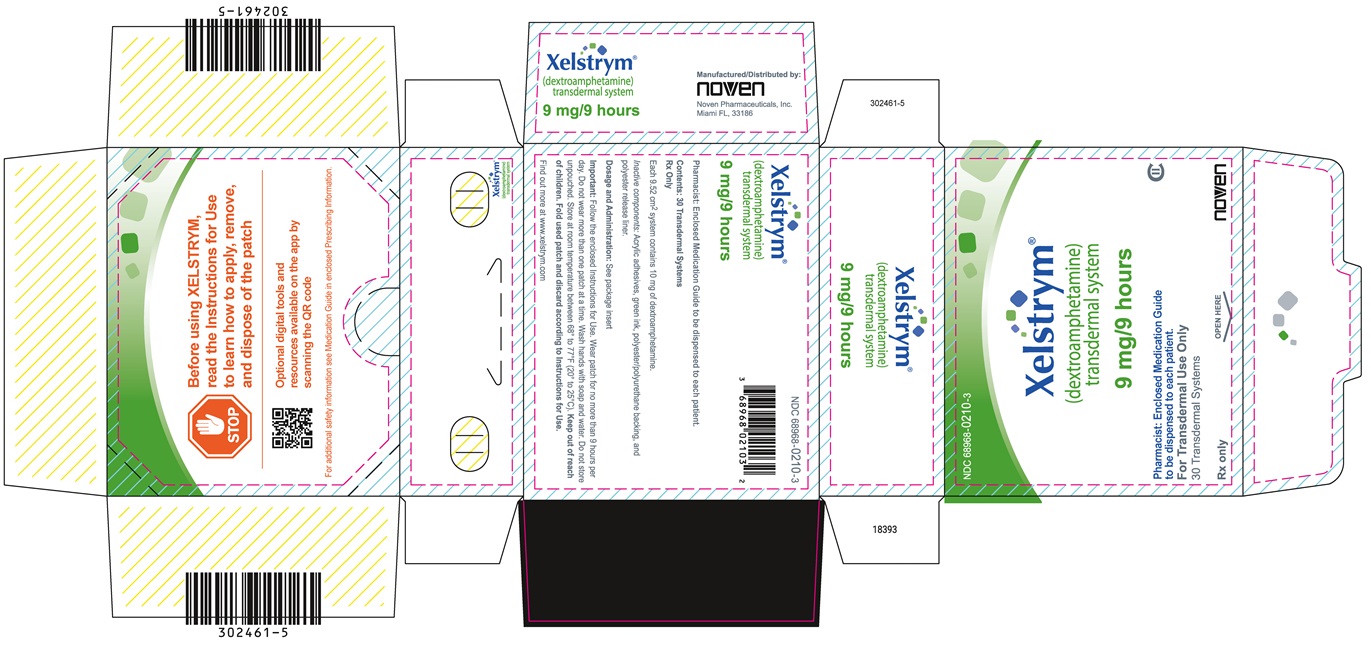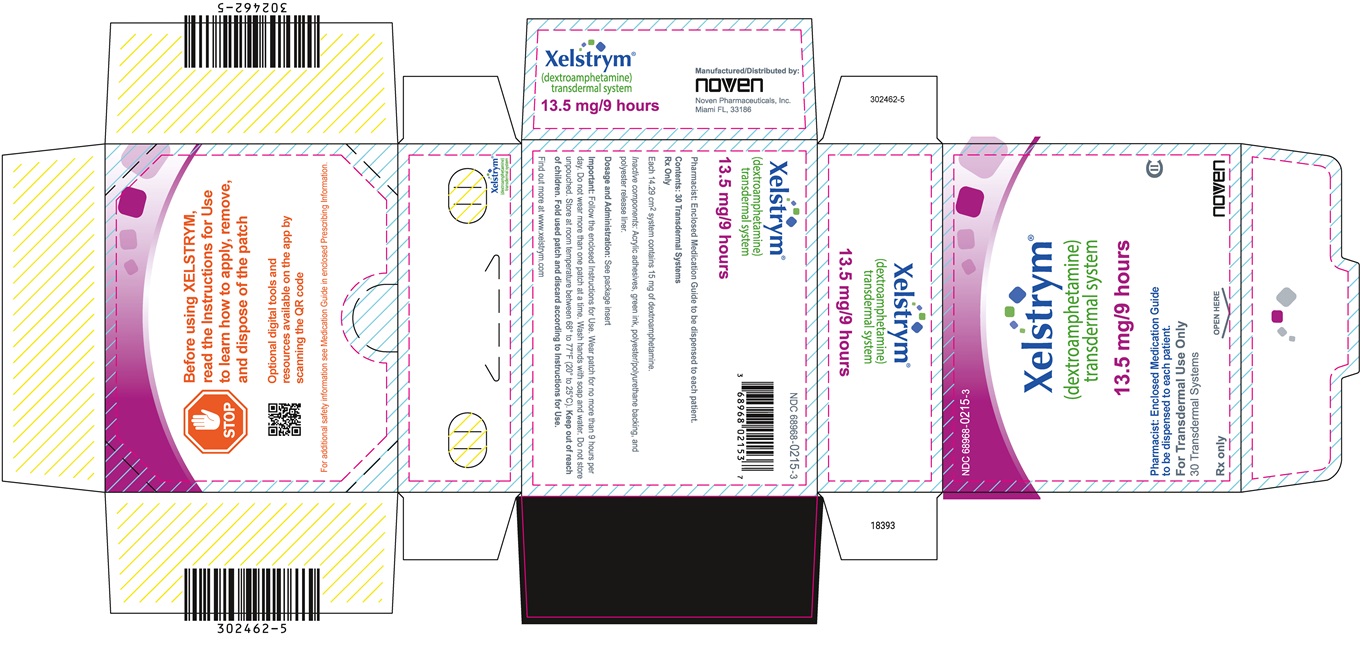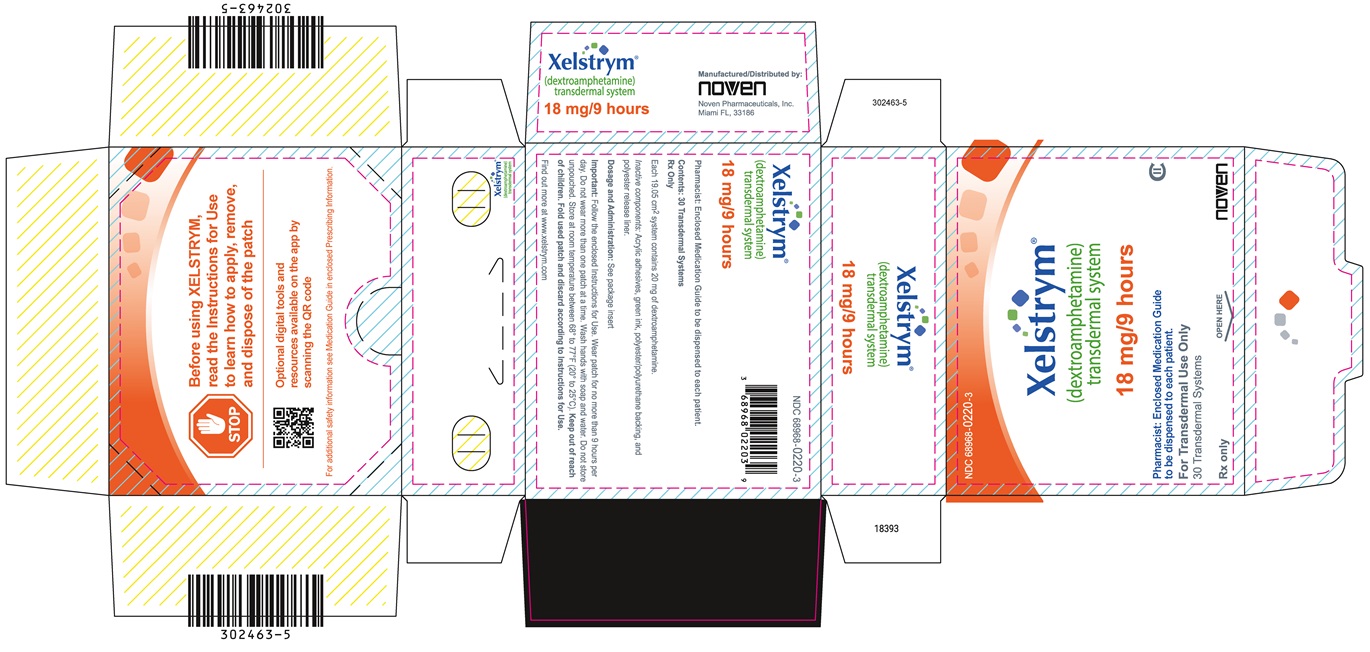 DRUG LABEL: XELSTRYM
NDC: 68968-0205 | Form: PATCH, EXTENDED RELEASE
Manufacturer: Noven Therapeutics, LLC
Category: prescription | Type: HUMAN PRESCRIPTION DRUG LABEL
Date: 20251223
DEA Schedule: CII

ACTIVE INGREDIENTS: DEXTROAMPHETAMINE 4.5 mg/1 1

HIGHLIGHTS OF PRESCRIBING INFORMATION

These highlights do not include all the information needed to use XELSTRYM safely and effectively. See full prescribing information for XELSTRYM.
XELSTRYM® (dextroamphetamine) transdermal system, CII
Initial U.S. Approval: 1975

WARNING: ABUSE, MISUSE, AND ADDICTION

See full prescribing information for complete boxed warning.

XELSTRYM has a high potential for abuse and misuse, which can lead to the development of a substance use disorder, including addiction. Misuse and abuse of CNS stimulants, including XELSTRYM, can result in overdose and death (5.1, 9.2, 10):

- Before prescribing XELSTRYM, assess each patient’s risk for abuse, misuse, and addiction.
- Educate patients and their families about these risks, proper storage of the drug, and proper disposal of any unused drug.
- Throughout treatment, reassess each patient’s risk and frequently monitor for signs and symptoms of abuse, misuse, and addiction.

RECENT MAJOR CHANGES

Indications and Usage | 09/2025
Warnings and Precautions (5.5) | 09/2025

1 INDICATIONS AND USAGE

XELSTRYM is a central nervous system (CNS) stimulant indicated for the treatment of Attention Deficit Hyperactivity Disorder (ADHD) in adults and pediatric patients 6 years and older (1)

Limitations of Use:

The use of XELSTRYM is not recommended in pediatric patients younger than 6 years of age because they had higher plasma exposure and a higher incidence of adverse reactions (e.g., weight loss) than patients 6 years and older at the same dosage (5.5, 8.4).

2 DOSAGE AND ADMINISTRATION

- Pediatric patients (6 to 17 years): Recommended starting dose is 4.5 mg/9 hours. Titrate dosage in weekly increments of 4.5 mg up to a maximum recommended dose of 18 mg/9 hours (2.2)
- Adults: Recommended starting dose is 9 mg/9 hours. Maximum recommended dose is 18 mg/9 hours (2.2)
- Apply one XELSTRYM transdermal system 2 hours before an effect is needed and remove within 9 hours (2.3)
- Apply XELSTRYM to one of the following sites: hip, upper arm, chest, upper back or flank. Change the site of application when applying a new transdermal system (2.3)
- Do not substitute for other amphetamine products on a milligram-per-milligram basis because of different amphetamine base compositions and differing pharmacokinetic profiles (2.5)
- Severe renal impairment: Maximum recommended dose is 13.5 mg/9 hours (2.6)
- End stage renal disease (ESRD): Maximum recommended dose is 9 mg/9 hours (2.6)

3 DOSAGE FORMS AND STRENGTHS

Transdermal system: 4.5 mg/9 hours, 9 mg/9 hours, 13.5 mg/9 hours, 18 mg/9 hours (3)

4 CONTRAINDICATIONS

- Known hypersensitivity to amphetamine products or other ingredients in XELSTRYM (4)
- Use with monoamine oxidase inhibitor (MAOI), or within 14 days of the last MAOI dose (4, 7.1)

5 WARNINGS AND PRECAUTIONS

- Risks to Patients with Serious Cardiac Disease: Avoid use in patients with known structural cardiac abnormalities, cardiomyopathy, serious cardiac arrhythmias, coronary artery disease, or other serious cardiac disease (5.2)
- Increased Blood Pressure and Heart Rate: Monitor blood pressure and pulse (5.3)
- Psychiatric Adverse Reactions: Prior to initiating XELSTRYM, screen patients for risk factors for developing a manic episode. If new psychotic or manic symptoms occur, consider discontinuing XELSTRYM (5.4)
- Long-Term Suppression of Growth in Pediatric Patients: Closely monitor growth (height and weight) in pediatric patients. Pediatric patients not growing or gaining height or weight as expected may need to have their treatment interrupted (5.5)
- Peripheral Vasculopathy, including Raynaud’s phenomenon: Careful observation for digital changes is necessary during XELSTRYM treatment. Further clinical evaluation (e.g., rheumatology referral) may be appropriate for patients who develop signs or symptoms of peripheral vasculopathy (5.6)
- Serotonin Syndrome: Increased risk when co-administered with serotonergic agents (e.g., SSRIs, SNRIs, triptans), but also during overdosage situations. If it occurs, discontinue XELSTRYM and initiate supportive treatment (5.7, 10)
- Contact Sensitization: Use of XELSTRYM may lead to contact sensitization. Discontinue XELSTRYM if contact sensitization is suspected (5.8)
- Application Site Reactions: During wear time or immediately after removal of XELSTRYM, local skin reactions may occur. Select a different application site each day to limit the occurrence of skin reactions (5.9)
- External Heat: Avoid exposing XELSTRYM to external heat sources during wear because both the rate and extent of absorption are increased (5.10)
- Motor and Verbal Tics, and Worsening of Tourette's Syndrome: Before initiating XELSTRYM, assess the family history and clinically evaluate patients for tics or Tourette’s syndrome. Regularly monitor patients for the emergence or worsening of tics or Tourette’s syndrome. Discontinue treatment if clinically appropriate (5.11)

6 ADVERSE REACTIONS

Most common adverse reactions (incidence ≥2% and greater than the rate for placebo) in pediatric patients 6 to 17 years treated with XELSTRYM were decreased appetite, headache, insomnia, tic, abdominal pain, vomiting, nausea, irritability, blood pressure increased, and heart rate increased (6.1)

Most common adverse reactions (incidence ≥5% and at a rate at least twice placebo) in adults treated with lisdexamfetamine were decreased appetite, insomnia, dry mouth, diarrhea, nausea, and anxiety (6.1)

To report SUSPECTED ADVERSE REACTIONS, contact Noven Therapeutics, LLC at 1-877-567-7857 or FDA at 1-800-FDA-1088 or www.fda.gov/medwatch.

7 DRUG INTERACTIONS

Acidifying and Alkalinizing Agents: Agents that alter GI and urinary pH can alter blood levels of amphetamine. Acidifying agents can decrease amphetamine blood levels, while alkalinizing agents increase amphetamine blood levels (2.7, 7.1)

8 USE IN SPECIFIC POPULATIONS

- Pregnancy: May cause fetal harm (8.1)
- Lactation: Breastfeeding not recommended (8.3)

FULL PRESCRIBING INFORMATION

WARNING: ABUSE, MISUSE, AND ADDICTION

XELSTRYM has a high potential for abuse and misuse, which can lead to the development of a substance use disorder, including addiction. Misuse and abuse of CNS stimulants, including XELSTRYM, can result in overdose and death [see OVERDOSAGE (10)], and this risk is increased with higher doses or unapproved methods of administration, such as snorting or injection.

Before prescribing XELSTRYM, assess each patient’s risk for abuse, misuse, and addiction. Educate patients and their families about these risks, proper storage of the drug, and proper disposal of any unused drug. Throughout XELSTRYM treatment, reassess each patient’s risk of abuse, misuse, and addiction and frequently monitor for signs and symptoms of abuse, misuse, and addiction [see WARNINGS AND PRECAUTIONS (5.1) and DRUG ABUSE AND DEPENDENCE (9.2)].

1 INDICATIONS AND USAGE

XELSTRYM® is indicated for the treatment of Attention Deficit Hyperactivity Disorder (ADHD) in adults and pediatric patients 6 years and older [see CLINICAL STUDIES (14)].

Limitations of Use

The use of XELSTRYM is not recommended in pediatric patients younger than 6 years of age because they had higher plasma exposure and a higher incidence of adverse reactions (e.g., weight loss) than patients 6 years and older at the same dosage [see Warnings and Precautions (5.5), Use in Specific Populations (8.4)].

2 DOSAGE AND ADMINISTRATION

2.1 Pretreatment Screening

Prior to treating patients with XELSTRYM, assess:

- for the presence of cardiac disease (i.e., perform a careful history, family history of sudden death or ventricular arrhythmia, and physical exam) [see WARNINGS AND PRECAUTIONS (5.2)].
- the family history and clinically evaluate patients for motor or verbal tics or Tourette’s syndrome before initiating XELSTRYM [see WARNINGS AND PRECAUTIONS (5.11)].

2.2 Recommended Dosage

Pediatric Patients 6 to 17 years

- Recommended starting dose of XELSTRYM in pediatric patients 6 to 17 years is 4.5 mg/9 hours. Dosage may be adjusted in weekly increments of 4.5 mg up to a maximum recommended dose of 18 mg/9 hours.

Adults

- Recommended starting dose of XELSTRYM in adults is 9 mg/9 hours. Dosage may be adjusted up to a maximum recommended dose of 18 mg/9 hours.

Apply XELSTRYM to the application site 2 hours before an effect is needed and remove within 9 hours after application. Dose titration and final dosage should be individualized depending on clinical response and tolerability.

2.3 Important Administration Instructions

- Apply one XELSTRYM transdermal system at a time for not more than 9 hours. Use only one XELSTRYM per 24 hours.
- Apply XELSTRYM to clean (void of lotions, oils, or gels), dry (not wet), and intact skin at the selected application site. Application sites include: hip, upper arm, chest, upper back, or flank. Select a different application site each time a new XELSTRYM transdermal system is applied [see WARNINGS AND PRECAUTIONS (5.9)].
- Avoid touching the adhesive side of XELSTRYM in order to avoid absorption of amphetamine. If the adhesive side is touched, immediately wash hands with soap and water.
- If the XELSTRYM transdermal system lifts at the edges, reattach XELSTRYM by pressing firmly and smoothing down the edges of the system. If XELSTRYM comes off completely, apply a new XELSTRYM transdermal system. XELSTRYM should not be applied or re-applied with dressings, tape or other common adhesives.
- Avoid exposing the application site to direct external heat sources, such as hair dryers, heating pads, electric blankets, heated water beds, etc., while wearing XELSTRYM [see WARNINGS AND PRECAUTIONS (5.10)]. When heat is applied to XELSTRYM after application, both the rate and the extent of absorption are increased [see CLINICAL PHARMACOLOGY (12.3)].

2.4 Switching from Other Amphetamine Products

For patients switching from another medication or any other amphetamine product, discontinue that treatment, and titrate with XELSTRYM using the titration schedule [see DOSAGE AND ADMINISTRATION (2.2)].

Do not substitute for other amphetamine products on a milligram-per-milligram basis because of different amphetamine base compositions and differing pharmacokinetic profiles [see CLINICAL PHARMACOLOGY (12.3)].

2.5 Dosage in Patients with Renal Impairment

In patients with severe renal impairment (GFR 15 to < 30 mL/min/1.73 m^2), the maximum dose should not exceed 13.5 mg/9 hours. The maximum recommended dose in end stage renal disease (GFR < 15 mL/min/1.73 m^2) patients is 9 mg/9 hours [see USE IN SPECIFIC POPULATIONS (8.6)].

2.6 Dosage Modification due to Drug Interactions

Agents that alter urinary pH can impact excretion and alter blood levels of amphetamines. Acidifying agents (e.g., ascorbic acid) decrease blood levels; adjust XELSTRYM dosage based on clinical response [see DRUG INTERACTIONS (7.1)].

3 DOSAGE FORMS AND STRENGTHS

XELSTRYM is a translucent transdermal system with a printed backing on one side and a release liner on the other that is available in four strengths:

- 4.5 mg dextroamphetamine/9 hours
- 9 mg dextroamphetamine/9 hours
- 13.5 mg dextroamphetamine/9 hours
- 18 mg dextroamphetamine/9 hours

4 CONTRAINDICATIONS

XELSTRYM is contraindicated in patients:

- with known hypersensitivity to amphetamine products or other components of XELSTRYM. Anaphylactic reactions, Stevens-Johnson Syndrome, angioedema, and urticaria have been observed in postmarketing reports [see ADVERSE REACTIONS (6.2)]
- taking monoamine oxidase inhibitors (MAOI), or within 14 days of stopping MAOIs (including MAOIs such as linezolid or intravenous methylene blue), because of an increased risk of hypertensive crisis [see WARNINGS AND PRECAUTIONS (5.7) and DRUG INTERACTIONS (7.1)]

5 WARNINGS AND PRECAUTIONS

5.1 Abuse, Misuse, and Addiction

XELSTRYM has a high potential for abuse and misuse. The use of XELSTRYM exposes individuals to the risks of abuse and misuse, which can lead to the development of a substance use disorder, including addiction. XELSTRYM can be diverted for non-medical use into illicit channels or distribution [see Drug Abuse and Dependence (9.2)]. Misuse and abuse of CNS stimulants, including XELSTRYM, can result in overdose and death [see Overdosage (10)], and this risk is increased with higher doses or unapproved methods of administration, such as snorting or injection.

Before prescribing XELSTRYM, assess each patient’s risk for abuse, misuse, and addiction. Educate patients and their families about these risks and proper disposal of any unused drug. Advise patients to store XELSTRYM in a safe place, preferably locked, and instruct patients to not give XELSTRYM to anyone else. Throughout XELSTRYM treatment, reassess each patient’s risk of abuse, misuse, and addiction and frequently monitor for signs and symptoms of abuse, misuse, and addiction.

5.2 Risks to Patients with Serious Cardiac Disease

Sudden death has been reported in patients with structural cardiac abnormalities or other serious cardiac disease who were treated with CNS stimulants at the recommended ADHD dosage.

Avoid XELSTRYM use in patients with known structural cardiac abnormalities, cardiomyopathy, serious cardiac arrhythmia, coronary artery disease, or other serious cardiac disease.

5.3 Increased Blood Pressure and Heart Rate

CNS stimulants cause an increase in blood pressure (mean increase about 2 to 4 mm Hg) and heart rate (mean increase about 3 to 6 bpm). Monitor all XELSTRYM-treated patients for potential tachycardia and hypertension.

5.4 Psychiatric Adverse Reactions

Exacerbation of Pre-existing Psychosis

CNS stimulants may exacerbate symptoms of behavior disturbance and thought disorder in patients with a pre-existing psychotic disorder.

Induction of a Manic Episode in Patients with Bipolar Disorder

CNS stimulants may induce a manic or mixed episode in patients. Prior to initiating XELSTRYM treatment, screen patients for risk factors for developing a manic episode (e.g., comorbid or history of depressive symptoms or a family history of suicide, bipolar disorder, and depression).

New Psychotic or Manic Symptoms

CNS stimulants, at the recommended dosage, may cause psychotic or manic symptoms (e.g., hallucinations, delusional thinking, or mania) in patients without a prior history of psychotic illness or mania. In a pooled analysis of multiple short-term, placebo-controlled studies of CNS stimulants, psychotic or manic symptoms occurred in approximately 0.1% of CNS stimulant-treated patients compared to 0% of placebo-treated patients. If such symptoms occur, consider discontinuing XELSTRYM.

5.5 Long-Term Suppression of Growth in Pediatric Patients

XELSTRYM is not approved for use and is not recommended in pediatric patients below 6 years of age [see Use in Specific Populations (8.4)].

CNS stimulants have been associated with weight loss and slowing of growth rate in pediatric patients. Closely monitor growth (weight and height) in XELSTRYM-treated pediatric patients treated with CNS stimulants, including XELSTRYM. In a 7-week trial with a dose-optimization phase and a placebo-controlled phase of XELSTRYM in pediatric patients 6 to 17 years old with ADHD, there was a mean decrease in weight while taking XELSTRYM. Additionally, in studies of another CNS stimulant, there was slowing of the increase in height [see ADVERSE REACTIONS (6.1)].

Pediatric patients not growing or gaining height or weight as expected may need to have their treatment interrupted. XELSTRYM is not approved for use in pediatric patients below 6 years of age [see USE IN SPECIFIC POPULATIONS (8.4)].

5.6 Peripheral Vasculopathy, including Raynaud’s Phenomenon

CNS stimulants, including XELSTRYM, used to treat ADHD are associated with peripheral vasculopathy, including Raynaud's phenomenon. Signs and symptoms are usually intermittent and mild; however, sequelae have included digital ulceration and/or soft tissue breakdown. Effects of peripheral vasculopathy, including Raynaud's phenomenon, were observed in post-marketing reports and at the therapeutic dosage of CNS stimulants in all age groups throughout the course of treatment. Signs and symptoms generally improved after dosage reduction or discontinuation of the CNS stimulant. Careful observation for digital changes is necessary during XELSTRYM treatment. Further clinical evaluation (e.g., rheumatology referral) may be appropriate for XELSTRYM-treated patients who develop signs or symptoms of peripheral vasculopathy.

5.7 Serotonin Syndrome

Serotonin syndrome, a potentially life-threatening reaction, may occur when amphetamines are used in combination with other drugs that affect the serotonergic neurotransmitter systems such as monoamine oxidase inhibitors (MAOIs), selective serotonin reuptake inhibitors (SSRIs), serotonin norepinephrine reuptake inhibitors (SNRIs), triptans, tricyclic antidepressants, fentanyl, lithium, tramadol, tryptophan, buspirone, and St. John's Wort [see DRUG INTERACTIONS (7.1)]. The co-administration with cytochrome P450 2D6 (CYP2D6) inhibitors may also increase the risk with increased exposure to XELSTRYM. In these situations, consider an alternative non-serotonergic drug or an alternative drug that does not inhibit CYP2D6 [see DRUG INTERACTIONS (7.1)].

Serotonin syndrome symptoms may include mental status changes (e.g., agitation, hallucinations, delirium, and coma), autonomic instability (e.g., tachycardia, labile blood pressure, dizziness, diaphoresis, flushing, hyperthermia), neuromuscular symptoms (e.g., tremor, rigidity, myoclonus, hyperreflexia, incoordination), seizures, and/or gastrointestinal symptoms (e.g., nausea, vomiting, diarrhea).

Concomitant use of XELSTRYM with MAOI drugs is contraindicated [see CONTRAINDICATIONS (4)].

Discontinue treatment with XELSTRYM and any concomitant serotonergic agents immediately if symptoms of serotonin syndrome occur, and initiate supportive symptomatic treatment. If concomitant use of XELSTRYM with other serotonergic drugs or CYP2D6 inhibitors is clinically warranted, initiate XELSTRYM with lower doses, monitoring patients for the emergence of serotonin syndrome during drug initiation or titration, and inform patients of the increased risk for serotonin syndrome.

5.8 Contact Sensitization

Use of XELSTRYM may lead to contact sensitization (allergic contact dermatitis). Erythema is commonly seen with use of XELSTRYM and is not by itself an indication of sensitization. However, contact sensitization should be suspected if erythema is accompanied by evidence of a more intense local reaction (edema, papules, vesicles) that does not significantly improve within 48 hours or spreads beyond the application site. Confirmation of a diagnosis of contact sensitization may require further diagnostic testing [see CONTRAINDICATION (4)].

Manifestations of systemic sensitization may include a flare-up of previous dermatitis or of prior positive patch-test sites, or generalized skin eruptions in previously unaffected skin. Other systemic reactions may include headache, fever, malaise, arthralgia, diarrhea, or vomiting. No cases of systemic sensitization have been observed in clinical trials of XELSTRYM.

Patients who develop contact sensitization to XELSTRYM and require oral treatment with amphetamine should be initiated on oral medication under close medical supervision. Discontinue XELSTRYM if contact sensitization is suspected. It is possible that some patients sensitized to amphetamine by exposure to XELSTRYM may not be able to take amphetamine in any form.

5.9 Application Site Reactions

Local skin reactions, such as pain, pruritus, burning sensation, erythema, discomfort, edema, and/or swelling were reported during the wear time or immediately after removal of XELSTRYM [see ADVERSE REACTIONS (6.1)]. Patients who experienced discomfort and/or pain during the wear time reported resolution within 2 to 4 hours after application.

The potential for application site reactions and increased skin irritation, discomfort or pain may occur with XELSTRYM if the same application site is used repeatedly. Patients should select a different application site each day to minimize skin reactions.

5.10 Use of External Heat

When heat is applied to XELSTRYM after application, both the rate and extent of absorption are increased. After application of a heating pad, amphetamine exposure (AUC0-9h) was about 1.5-times greater than without heating pad application [see CLINICAL PHARMACOLOGY (12.3)]. Advise patients to avoid exposing XELSTRYM to direct external heat sources such as hair dryers, heating pads, electric blankets, heated water beds, etc., while wearing XELSTRYM.

5.11 Motor and Verbal Tics, and Worsening of Tourette’s Syndrome

CNS stimulants, including amphetamine, have been associated with the onset or exacerbation of motor and verbal tics. Worsening of Tourette’s syndrome has also been reported [see ADVERSE REACTIONS (6.2)].

Before initiating XELSTRYM, assess the family history and clinically evaluate patients for tics or Tourette’s syndrome. Regularly monitor XELSTRYM-treated patients for the emergence or worsening of tics or Tourette’s syndrome, and discontinue treatment if clinically appropriate.

6 ADVERSE REACTIONS

The following adverse reactions are discussed in greater detail in other sections of the labeling

- Known hypersensitivity to amphetamine products or other ingredients of XELSTRYM [see CONTRAINDICATIONS (4)]
- Hypertensive Crisis When Used Concomitantly with Monoamine Oxidase Inhibitors [see CONTRAINDICATIONS (4) and DRUG INTERACTIONS (7.1)]
- Abuse, Misuse, and Addiction [see BOXED WARNING, WARNINGS AND PRECAUTIONS (5.1) and DRUG ABUSE AND DEPENDENCE (9.2, 9.3)]
- Risks to Patients with Serious Cardiac Disease [see WARNINGS AND PRECAUTIONS (5.2)]
- Increased Blood Pressure and Heart Rate [see WARNINGS AND PRECAUTIONS (5.3)]
- Psychiatric Adverse Reactions [see WARNINGS AND PRECAUTIONS (5.4)]
- Long-Term Suppression of Growth in Pediatric Patients [see WARNINGS AND PRECAUTIONS (5.5)]
- Peripheral Vasculopathy, including Raynaud's phenomenon [see WARNINGS AND PRECAUTIONS (5.6)]
- Serotonin Syndrome [see WARNINGS AND PRECAUTIONS (5.7)]
- Contact Sensitization [see WARNINGS AND PRECAUTIONS (5.8)]
- Application Site Reactions [see WARNINGS AND PRECAUTIONS (5.9)]
- Use of External Heat [see WARNINGS AND PRECAUTIONS (5.10)]
- Motor and Verbal Tics, and Worsening of Tourette’s Syndrome [see WARNINGS AND PRECAUTIONS (5.11)]

6.1 Clinical Trial Experience

Because clinical trials are conducted under widely varying conditions, adverse reaction rates observed in the clinical trials of a drug cannot be directly compared to rates in the clinical trials of another drug and may not reflect the rates observed in clinical practice.

The safety of XELSTRYM for the treatment of ADHD in adults and pediatric patients 6 to 17 years is based on a study with XELSTRYM in pediatric patients (presented below) and adequate and well-controlled studies of lisdexamfetamine in adult and pediatric patients with ADHD.

XELSTRYM was studied in pediatric patients 6 to 17 years with ADHD. The safety data are from a 7-week study including a 5-week open-label dose optimization phase (n=110) followed by a 2-week randomized, parallel-group, crossover, placebo-controlled double-blind treatment phase (n=105) [see CLINICAL TRIALS (14)].

Adverse Reactions Leading to Discontinuation of Treatment

In the dose-optimization phase (no placebo comparator in this phase), 2.7% (3/110) of patients treated with XELSTRYM discontinued due to adverse reactions. These adverse reactions reported in one patient each were abdominal pain (0.9%), irritability (0.9%) and decreased appetite (0.9%). There were no discontinuations due to adverse reactions during the double-blind phase.

Adverse Reactions Occurring at an Incidence of 5% or More in XELSTRYM Treated Pediatric Patients Ages 6 to 17 Years During Dose-optimized Treatment

Adverse reactions (incidence of ≥ 5%) that occurred during the dose-optimization phase of the clinical study include: decreased appetite (54%), insomnia^1 (32%), headache (21%), irritability (16%), abdominal pain^2 (16%) affect lability^3 (16%), application site pain^4 (13%), nausea (9%), application site pruritus (7%), and fatigue (5%).

^1insomnia includes insomnia, delayed sleep phase, initial insomnia, middle insomnia, and terminal insomnia
^2abdominal pain includes abdominal pain and abdominal pain upper
^3affect lability includes affect lability, emotional disorder, mood swings, and mood altered
^4application site pain includes application site pain and application site burn

Adverse Reactions Occurring at an Incidence of 2% or More of XELSTRYM-Treated Pediatric Patients Ages 6 to 17 Years During Double-blind Treatment

Adverse reactions (incidence of ≥ 2% and incidence greater than placebo) that occurred during the double-blind, placebo-controlled phase of the clinical study are shown in Table 1.

Table 1: Adverse Reactions Reported by ≥ 2% of Pediatric Patients 6 to 17 Years with ADHD Receiving XELSTRYM and Greater Incidence Than Placebo in the Double-Blind Phase

System Organ Class Preferred Term | XELSTRYM All Doses (n = 105) % | Placebo (n = 105) %
Metabolism and nutrition disorders
Decreased appetite | 12 | 2
Nervous system disorders
Headache | 6 | 4
Psychiatric disorders
Insomnia* | 8 | 6
Affect lability | 3 | 0
Tic | 2 | 0
Gastrointestinal Disorders
Vomiting | 4 | 0
Abdominal pain* | 4 | 2
Nausea | 3 | 1
General disorders and administration site conditions
Irritability | 2 | 1
Investigations/Cardiac Disorders
Blood pressure increased* | 2 | 1
Heart rate increased* | 2 | 0
*The following terms were combined:
Insomnia includes insomnia, delayed sleep phase, initial insomnia, middle insomnia, and terminal insomnia
Abdominal pain includes abdominal pain and abdominal pain upper
Blood pressure increased includes blood pressure increased and blood pressure systolic increased
Heart rate increased includes heart rate increased and tachycardia

Application Site Reactions

Based on daily patient diaries and dermal reaction scales at clinic assessments, local skin reactions were reported with XELSTRYM. During the wear time or immediately after removal of XELSTRYM, patients experienced pain, pruritus, burning sensation, erythema, discomfort, edema, and swelling.

Patients who experienced discomfort and pain at the application site during the wear time reported resolution within 2 to 4 hours after XELSTRYM application. Most dermal irritation was limited to the site of application. All patients who reported application site reactions in the 7-week pediatric classroom study continued to use XELSTRYM, and there were no discontinuations from the study due to application site reactions.

During the dose-optimization phase of the clinical study, 45% of patients reported application site discomfort associated with the use of XELSTRYM in daily patient diaries; 72% of patients reported discomfort at clinic visit assessments; and 13% of patients reported severe discomfort at clinic visit assessments. XELSTRYM 4.5 mg was the starting dose for all patients undergoing titration during the dose optimization phase and the majority of application site discomfort was reported at this starting dose. During the dose-optimization phase, 73% of patients reported application site irritation.

Application site reactions that occurred during the double-blind phase of the clinical study are presented in Table 2.

Table 2: Summary Application Site Reactions During the Double-Blind Phase

 | XELSTRYM n/N | Placebo n/N
Discomfort
Reported in patient diaries | 8/96 (8%) | 8/98 (8%)
Clinic assessments
Any discomfort | 72/104 (69%) | 9/101 (9%)
Severe discomfort | 10/104 (10%) | 4/101 (4%)
Irritation
Reported in patient diaries | 64/103 (62%) | 41/105 (39%)
Reported at Clinic assessments | 97/103 (94%) | 55/101 (54%)

Weight Loss and Slowing Growth Rate

In a 7-week trial of XELSTRYM with a 5-week dose optimization phase and a 2-week crossover placebo-controlled phase in pediatric patients ages 6 to 17 years, patients had a mean weight loss from baseline of -3.1 pounds after 5 weeks of XELSTRYM.

Leukopenia and Neutropenia

In the 2-week crossover phase of the 7-week trial of XELSTRYM in pediatric patients ages 6 to 17 years, shifts in WBCs from normal to low occurred in 10% of patients treated with XELSTRYM and 2% of patients treated with placebo. Shifts in neutrophils from normal to low occurred in 14% of patients treated with XELSTRYM and 6% of patients treated with placebo.

Weight Loss and Slowing Growth Rate in Pediatric Patients with ADHD with Lisdexamfetamine and Other Stimulants

Lisdexamfetamine

The long-term safety of XELSTRYM for the treatment of ADHD relies on information from adequate and well-controlled studies of lisdexamfetamine. In a controlled trial of lisdexamfetamine in pediatric patients 6 to 12 years, mean weight loss from baseline after 4 weeks of therapy was -0.9, -1.9, and -2.5 pounds, respectively, for patients receiving 30 mg, 50 mg, and 70 mg of lisdexamfetamine, compared to 1 pound weight gain for patients receiving placebo. Higher doses were associated with greater weight loss with 4 weeks of treatment. Careful follow-up for weight in pediatric patients 6 to 12 years who received lisdexamfetamine over 12 months suggests that consistently medicated pediatric patients (i.e., treatment for 7 days per week throughout the year) have a slowing in growth rate, measured by body weight as demonstrated by an age- and sex-normalized mean change from baseline in percentile, of -13.4 over 1 year (average percentiles at baseline and 12 months were 60.9 and 47.2, respectively). In a 4-week controlled trial of lisdexamfetamine in pediatric patients 13 to 17 years, mean weight loss from baseline to endpoint was -2.7, -4.3, and -4.8 pounds, respectively, for patients receiving 30 mg, 50 mg, and 70 mg of lisdexamfetamine, compared to a 2 pound weight gain for patients receiving placebo.

Other CNS stimulants

Careful follow-up of weight and height in pediatric patients 7 to 10 years who were randomized to either methylphenidate or non-medication treatment groups over 14 months, as well as in naturalistic subgroups of newly methylphenidate-treated and non-medication treated pediatric patients over 36 months (to the ages of 10 to 13 years), suggests that consistently medicated pediatric patients 7 to 13 years (i.e., treatment for 7 days per week throughout the year) have a temporary slowing in growth rate (on average, a total of about 2 cm less growth in height and 2.7 kg less growth in weight over 3 years), without evidence of growth rebound during this period of development. In a controlled trial of amphetamine (d- and l-enantiomer ration of 3:1) in pediatric patients 13 to 17 years, mean weight change from baseline within the initial 4 weeks of therapy was -1.1 pounds and -2.8 pounds, respectively, for patients receiving 10 mg and 20 mg of amphetamine. Higher doses were associated with greater weight loss within the initial 4 weeks of treatment [see WARNINGS AND PRECAUTIONS (5.5)].

Clinical Trials Experience in Adult Patients with ADHD Treated with Lisdexamfetamine

Adverse Reactions Associated with Discontinuation of Treatment in Adult ADHD Clinical Trials

In a controlled trial of lisdexamfetamine in adults with ADHD, 6% (21/358) of lisdexamfetamine-treated patients discontinued due to adverse reactions compared to 2% (1/62) of placebo-treated patients. The most frequently reported adverse reactions (1% or more and twice rate of placebo) were insomnia (8/358; 2%), tachycardia (3/358; 1%), irritability (2/358; 1%), hypertension (4/358; 1%), headache (2/358; 1%), anxiety (2/358; 1%), and dyspnea (3/358; 1%). Less frequently reported adverse reactions (less than 1% or less than twice rate of placebo) included palpitations, diarrhea, nausea, decreased appetite, dizziness, agitation, depression, paranoia and restlessness.

Adverse Reactions Occurring at an Incidence of ≥5% or More Among Lisdexamfetamine-Treated Patients with ADHD in Clinical Trials

The most common adverse reactions (incidence ≥5% and at a rate at least twice placebo) were: Decreased appetite, insomnia, dry mouth, diarrhea, nausea, and anxiety.

In addition, in the adult population, erectile dysfunction was observed in 2.6% of males on lisdexamfetamine and 0% on placebo; decreased libido was observed in 1.4% of subjects on lisdexamfetamine and 0% on placebo.

Weight Loss in Adults with ADHD

In a controlled adult trial of lisdexamfetamine, mean weight loss after 4 weeks of therapy was 2.8 pounds, 3.1 pounds, and 4.3 pounds, for patients receiving final doses of 30 mg, 50 mg, and 70 mg of lisdexamfetamine, respectively, compared to a mean weight gain of 0.5 pounds for patients receiving placebo.

Adverse Reactions with Other Amphetamine Products in Pediatric Patients and Adults with ADHD

Cardiac Disorders: Palpitations, tachycardia, and chest pain.

Gastrointestinal Disorders: Dry mouth, abdominal pain upper, dyspepsia, diarrhea, constipation, vomiting, nausea, and tooth disorder (e.g., teeth clenching, tooth infection).

General Disorders and Administration Site Conditions: Asthenia, fatigue, pyrexia, and feeling jittery.

Infections and Infestations: Infection, urinary tract infection.

Injury, Poisoning, and Procedural Complications: Accidental injury.

Investigations: Weight decreased, blood pressure increased, and ECG voltage criteria for ventricular hypertrophy.

Metabolism and Nutrition Disorders: Loss of appetite.

Musculoskeletal and Connective Tissue Disorders: Muscle twitching, growth retardation.

Nervous System Disorders: Somnolence, insomnia, tremor, dizziness, headache, tics, speech disorder (e.g., stuttering, excessive speech), psychomotor hyperactivity, and agitation.

Psychiatric Disorders: Depression, anxiety, dermatillomania, mood swings, anger, affect lability, logorrhea, irritability, nervousness, paranoia, and restlessness.

Reproductive System and Breast Disorders: Impotence, libido decreased, erectile dysfunction, and dysmenorrhea.

Respiratory, Thoracic, and Mediastinal Disorders: Dyspnea, rhinitis allergic.

Skin and Subcutaneous Tissue Disorders: Rash, photosensitivity reaction, and hyperhidrosis.

Vascular Disorders: Hypertension, epistaxis.

6.2 Postmarketing Experience

The following adverse reactions have been identified during post-approval use of amphetamines. Because these reactions are reported voluntarily from a population of uncertain size, it is not always possible to reliably estimate their frequency or establish a causal relationship to drug exposure.

Cardiac Disorders: Palpitations, chest pain, sudden death, and myocardial infarction. There have been isolated reports of cardiomyopathy associated with chronic amphetamine use.

Eye Disorders: Vision blurred, diplopia, difficulties with visual accommodation, and mydriasis.

Gastrointestinal Disorders: Dysgeusia, constipation, intestinal ischemia, and other gastrointestinal disturbances.

Hepatobiliary Disorders: Eosinophilic hepatitis.

Immune System Disorders: Urticaria, rash, hypersensitivity reactions including angioedema and anaphylactic reaction. Serious skin rashes, including Stevens-Johnson Syndrome and toxic epidermal necrolysis, have been reported.

Musculoskeletal and Connective Tissue Disorders: Rhabdomyolysis.

Nervous System Disorders: Seizures, overstimulation, restlessness, dyskinesia, tremor, motor and verbal tics, and paresthesia (including formication).

Psychiatric Disorders: Psychotic episodes at recommended doses, depression, logorrhea, aggression, anger, dermatillomania, bruxism, dysphoria, euphoria, and irritability.

Reproductive System and Breast Disorders: Impotence, changes in libido, and frequent or prolonged erections.

Skin and Subcutaneous Tissue Disorders: Alopecia.

Vascular Disorders: Raynaud's phenomenon.

7 DRUG INTERACTIONS

7.1 Drugs Having Clinically Important Interactions with Amphetamine

Table 3: Drugs Having Clinically Important Interactions with Amphetamines

MAO Inhibitors (MAOI)
Clinical Impact | MAOI antidepressants slow amphetamine metabolism, increasing amphetamine’s effect on the release of norepinephrine and other monoamines from adrenergic nerve endings causing headaches and other signs of hypertensive crisis. Toxic neurological effects and malignant hyperpyrexia can occur, sometimes with fatal results.
Intervention | Do not administer XELSTRYM during or within 14 days following the administration of MAOI [see CONTRAINDICATIONS (4) and WARNINGS AND PRECAUTIONS (5.7)].
Serotonergic Drugs
Clinical Impact | The concomitant use of XELSTRYM and serotonergic drugs increases the risk of serotonin syndrome.
Intervention | Initiate with lower doses and monitor patients for signs and symptoms of serotonin syndrome, particularly during XELSTRYM initiation or dosage increase. If serotonin syndrome occurs, discontinue XELSTRYM and the concomitant serotonergic drug(s) [see WARNINGS AND PRECAUTIONS (5.7)].
CYP2D6 Inhibitors
Clinical Impact | The concomitant use of XELSTRYM and CYP2D6 inhibitors may increase the exposure of XELSTRYM compared to the use of the drug alone, and increase the risk of serotonin syndrome.
Intervention | Initiate with lower doses and monitor patients for signs and symptoms of serotonin syndrome, particularly during XELSTRYM initiation and after a dosage increase. If serotonin syndrome occurs, discontinue XELSTRYM and the CYP2D6 inhibitor [see WARNINGS AND PRECAUTIONS (5.7) and OVERDOSAGE (10)].
Alkalinizing Agents
Clinical Impact | Urinary alkalinizing agents can increase blood levels and potentiate the action of amphetamine.
Intervention | Co-administration of XELSTRYM and urinary alkalinizing agents should be avoided.
Acidifying Agents
Clinical Impact | Urinary acidifying agents can lower blood levels and efficacy of amphetamines.
Intervention | Increase dose based on clinical response.
Tricyclic Antidepressants
Clinical Impact | May enhance the activity of tricyclic or sympathomimetic agents causing striking and sustained increases in the concentration of dextroamphetamine in the brain; cardiovascular effects can be potentiated.
Intervention | Monitor frequently and adjust or use alternative therapy based on clinical response.

7.2 Drugs Having No Clinically Important Interactions with Amphetamine

From a pharmacokinetic perspective, no dose adjustment of XELSTRYM is necessary when XELSTRYM is co-administered with guanfacine, venlafaxine, or omeprazole. In addition, no dose adjustment of guanfacine or venlafaxine is needed when XELSTRYM is co-administered [see CLINICAL PHARMACOLOGY (12.3)].

From a pharmacokinetic perspective, no dose adjustment for drugs that are substrates of CYP1A2 (e.g. theophylline, duloxetine, melatonin), CYP2D6 (e.g. atomoxetine, desipramine, venlafaxine), CYP2C19 (e.g. omeprazole, lansoprazole, clobazam), and CYP3A4 (e.g. midazolam, pimozide, simvastatin) is necessary when XELSTRYM is co-administered [see CLINICAL PHARMACOLOGY (12.3)].

8 USE IN SPECIFIC POPULATIONS

8.1 Pregnancy

Pregnancy Exposure Registry

There is a pregnancy exposure registry that monitors pregnancy outcomes in women exposed to ADHD medications, including XELSTRYM, during pregnancy. Healthcare providers are encouraged to register patients by calling the National Pregnancy Registry for Psychiatric Medications at 1-866-961-2388 or visiting online at https://womensmentalhealth.org/research/pregnancyregistry/adhd-medications/.

Risk Summary

Available data from published epidemiologic studies and postmarketing reports on use of prescription amphetamine in pregnant women have not identified a drug-associated risk of major birth defects and miscarriage (see DATA). Adverse pregnancy outcomes, including premature delivery and low birth weight, have been seen in infants born to mothers taking amphetamines during pregnancy [see CLINICAL CONSIDERATIONS].

No apparent effects on morphological development were observed in embryo-fetal development studies, with oral administration of amphetamine to rats and rabbits during organogenesis. However, in a pre- and post-natal development study, amphetamine (d- to l- ratio of 3:1) administered orally to pregnant rats during gestation and lactation caused a decrease in pup survival and a decrease in pup body weight that correlated with a delay in developmental landmarks at clinically relevant doses of amphetamine. In addition, adverse effects on reproductive performance were observed in pups whose mothers were treated with amphetamine. Long-term neurochemical and behavioral effects have also been reported in animal developmental studies using clinically relevant doses of amphetamine (see DATA).

The estimated background risk of major birth defects and miscarriage for the indicated population is unknown. All pregnancies have a background risk of birth defect, loss, or other adverse outcomes. In the U.S. general population, the estimated background risk of major birth defects and miscarriage in clinically recognized pregnancies is 2 to 4% and 15 to 20%, respectively.

Clinical Considerations

Fetal/Neonatal Adverse Reactions

Amphetamines, such as XELSTRYM, cause vasoconstriction and thereby may decrease placental perfusion. In addition, amphetamines can stimulate uterine contractions, increasing the risk of premature delivery. Infants born to mothers taking amphetamines during pregnancy have an increased risk of premature delivery and low birth weight.

Monitor infants born to mothers taking amphetamines for symptoms of withdrawal such as feeding difficulties, irritability, agitation, and excessive drowsiness.

Data

Animal Data

Amphetamine (d- to l- enantiomer ratio of 3:1) had no apparent effects on embryofetal morphological development or survival when administered orally to pregnant rats and rabbits throughout the period of organogenesis at doses of up to 6 and 16 mg/kg/day, respectively. Fetal malformations and death have been reported in mice following parenteral administration of amphetamine doses of 50 mg/kg/day or greater to pregnant animals. Administration of these doses was also associated with severe maternal toxicity.

A study was conducted in which pregnant rats received daily oral doses of amphetamine (d- to l- enantiomer ratio of 3:1) of 2, 6, and 10 mg/kg from gestation day 6 to lactation day 20. All doses caused hyperactivity and decreased weight gain in the dams. A decrease in pup survival was seen at all doses. A decrease in pup body weight was seen at 6 and 10 mg/kg which correlated with delays in developmental landmarks, such as preputial separation and vaginal opening. Increased pup locomotor activity was seen at 10 mg/kg on day 22 postpartum but not at 5 weeks postweaning. When pups were tested for reproductive performance at maturation, gestational weight gain, number of implantations, and number of delivered pups were decreased in the group whose mothers had been given 10 mg/kg.

A number of studies from the literature in rodents indicate that prenatal or early postnatal exposure to amphetamine (d- or d, l-) at doses similar to those used clinically can result in long-term neurochemical and behavioral alterations. Reported behavioral effects include learning and memory deficits, altered locomotor activity, and changes in sexual function.

8.2 Lactation

Risk Summary

Based on limited case reports in published literature, amphetamine (d- or d, l-) is present in human milk, at relative infant doses of 2% to 13.8% of the maternal weight-adjusted dosage and a milk/plasma ratio ranging between 1.9 and 7.5. There are no reports of adverse effects on the breastfed infant. Long-term neurodevelopmental effects on infants from amphetamine exposure are unknown. It is possible that large dosages of amphetamine might interfere with milk production, especially in women whose lactation is not well established. Because of the potential for serious adverse reactions in nursing infants, including serious cardiovascular reactions, blood pressure and heart rate increase, suppression of growth, and peripheral vasculopathy, advise patients that breastfeeding is not recommended during treatment with XELSTRYM.

8.4 Pediatric Use

The safety and effectiveness of XELSTRYM have not been established in pediatric patients below the age of 6 years.

The safety and effectiveness of XELSTRYM have been established in pediatric patients with ADHD ages 6 to 17 years [see ADVERSE REACTIONS (6.1), CLINICAL PHARMACOLOGY (12.3), and CLINICAL STUDIES (14)].

Safety and efficacy of lisdexamfetamine were evaluated in a double-blind, randomized, parallel-group, placebo-controlled, fixed-dose study in pediatric patients 4 to 5 years with ADHD, followed by a 1-year open-label extension study. In these studies, patients experienced elevated rates of adverse reactions, including weight loss, decreased BMI, decreased appetite, insomnia, infections (upper respiratory and nasopharyngitis), irritability, and affect lability.

Growth Suppression

Growth should be monitored during treatment with stimulants, including XELSTRYM, and pediatric patients who are not growing or gaining weight as expected may need to have their treatment interrupted [see WARNINGS AND PRECAUTIONS (5.5) and ADVERSE REACTIONS (6.1)].

Juvenile Animal Data

Juvenile rats treated with mixed amphetamine salts early in the postnatal period through sexual maturation demonstrated transient changes in motor activity. Learning and memory were impaired. No recovery was seen following a drug free period. A delay in sexual maturation was observed, although there was no effect on fertility.

In a juvenile developmental study, rats received daily oral doses of amphetamine (d- to l- enantiomer ratio of 3:1) of 2, 6, or 20 mg/kg on days 7-13 of age; from day 14 to approximately day 60 of age, these doses were given twice daily for total daily doses of 4, 12, or 40 mg/kg. Post dosing hyperactivity was seen at all doses; motor activity measured prior to the daily dose was decreased during the dosing period but the decreased motor activity was largely absent after an 18 day drug-free recovery period. Performance in the Morris water maze test for learning and memory was impaired at the 40 mg/kg dose, and sporadically at the lower doses, when measured prior to the daily dose during the treatment period; no recovery was seen after a 19 day drug-free period. A delay in the developmental milestones of vaginal opening and preputial separation was seen at 40 mg/kg but there was no effect on fertility.

8.5 Geriatric Use

Clinical studies of XELSTRYM did not include subjects over 65 years to determine whether they respond differently from younger subjects.

Other reported clinical experience and pharmacokinetic data [see CLINICAL PHARMACOLOGY (12.3)] have not identified differences in responses between the elderly and younger patients. In general, dose selection for an elderly patient should start at the low end of the dosing range, reflecting the greater frequency of decreased hepatic, renal, or cardiac function, and of concomitant disease or other drug therapy.

8.6 Renal Impairment

Due to reduced clearance in patients with severe renal impairment (GFR 15 to < 30 mL/min/1.73 m^2), the maximum XELSTRYM dose should not exceed 13.5 mg/9 hours. The maximum recommended dose in end stage renal disease (GFR < 15 mL/min/1.73 m^2) patients is 9 mg/9 hours XELSTRYM.

Dextroamphetamine is not dialyzable.

9 DRUG ABUSE AND DEPENDENCE

9.1 Controlled Substance

XELSTRYM contains dextroamphetamine, a Schedule II controlled substance.

9.2 Abuse

XELSTRYM has a high potential for abuse and misuse which can lead to the development of a substance use disorder, including addiction [see WARNINGS AND PRECAUTIONS (5.1)]. XELSTRYM can be diverted for non-medical use into illicit channels or distribution.

Abuse is the intentional non-therapeutic use of a drug, even once, to achieve a desired psychological or physiological effect. Misuse is the intentional use, for therapeutic purposes, of a drug by an individual in a way other than prescribed by a health care provider or for whom it was not prescribed. Drug addiction is a cluster of behavioral, cognitive, and physiological phenomena that may include a strong desire to take the drug, difficulties in controlling drug use (e.g., continuing drug use despite harmful consequences, giving a higher priority to drug use than other activities and obligations), and possible tolerance or physical dependence.

Misuse and abuse of dextroamphetamine may cause increased heart rate, respiratory rate, or blood pressure; sweating; dilated pupils; hyperactivity; restlessness; insomnia; decreased appetite; loss of coordination; tremors; flushed skin; vomiting; and/or abdominal pain. Anxiety, psychosis, hostility, aggression, and suicidal or homicidal ideation have also been observed with CNS stimulants abuse and/or misuse. Misuse and abuse of CNS stimulants, including XELSTRYM, can result in overdose and death [see OVERDOSAGE (10)], and this risk is increased with higher doses or unapproved methods of administration, such as snorting or injection.

9.3 Dependence

Physical Dependence

XELSTRYM may produce physical dependence. Physical dependence is a state that develops as a result of physiological adaptation in response to repeated drug use, manifested by withdrawal signs and symptoms after abrupt discontinuation or a significant dose reduction of a drug.

Withdrawal signs and symptoms after abrupt discontinuation or dose reduction following prolonged use of CNS stimulants including XELSTRYM include dysphoric mood; depression; fatigue; vivid, unpleasant dreams; insomnia or hypersomnia; increased appetite; and psychomotor retardation or agitation.

Tolerance

XELSTRYM may produce tolerance. Tolerance is a physiological state characterized by a reduced response to a drug after repeated administration (i.e., a higher dose of a drug is required to produce the same effect that was once obtained at a lower dose).

10 OVERDOSAGE

Clinical Effects of Overdose

Overdose of CNS stimulants is characterized by the following sympathomimetic effects:

- Cardiovascular effects including tachyarrhythmias, and hypertension or hypotension. Vasospasm, myocardial infarction, or aortic dissection may precipitate sudden cardiac death. Takotsubo cardiomyopathy may develop.
- CNS effects including psychomotor agitation, confusion, and hallucinations. Serotonin syndrome, seizures, cerebral vascular accidents, and coma may occur.
- Life-threatening hyperthermia (temperatures greater than 104°F) and rhabdomyolysis may develop.

Overdose Management

Consider the possibility of multiple drug ingestion. Dextroamphetamine is not dialyzable. Remove all transdermal systems immediately and cleanse the area(s) to remove any remaining adhesive. The continuing absorption of dextroamphetamine from the skin, even after removal of the transdermal system, should be considered when treating patients with overdose.

Consider contacting the Poison Help line (1-800-222-1222) or a medical toxicologist for additional overdose management recommendations.

11 DESCRIPTION

XELSTRYM (dextroamphetamine) transdermal system, contains dextroamphetamine, a CNS stimulant.

Dextroamphetamine is the dextro isomer of the compound d,l-amphetamine. The chemical name for dextroamphetamine is (2S)-1-phenylpropan-2-amine. It is a clear to slightly amber colored liquid. Molecular weight of dextroamphetamine is 135.21 g/mol and the molecular formula is C9H13N. The chemical structure is:

XELSTRYM is provided in four strengths: 4.5 mg/9 hours, 9 mg/9 hours, 13.5 mg/9 hours, and 18 mg/9 hours. The composition per unit area of all dosage strengths is identical. Inactive ingredients include: acrylic adhesives, green ink, polyester/polyurethane backing, and polyester release liner.

Table 4: XELSTRYM (dextroamphetamine) transdermal system

Dosage Strength (dextroamphetamine) | Dextroamphetamine Content per Transdermal System | Transdermal System Size
4.5 mg / 9 hours | 5 mg | 4.76 cm^2
9 mg / 9 hours | 10 mg | 9.52 cm^2
13.5 mg / 9 hours | 15 mg | 14.29 cm^2
18 mg / 9 hours | 20 mg | 19.05 cm^2

Transdermal System Components

XELSTRYM consists of three layers (Figure 1). The layers are (1) oversized protective silicone-coated polyester release liner that is removed and discarded prior to application (2) acrylic adhesive matrix containing dextroamphetamine, and (3) polyester and polyurethane laminate film (backing).

Figure 1: XELSTRYM Transdermal System (Exploded View)

12 CLINICAL PHARMACOLOGY

12.1 Mechanism of Action

Amphetamines are non-catecholamine sympathomimetic amines with CNS stimulant activity. The exact mode of therapeutic action in ADHD is not known.

12.2 Pharmacodynamics

Amphetamines block the reuptake of norepinephrine and dopamine into the presynaptic neuron and increase the release of these monoamines into the extraneuronal space.

12.3 Pharmacokinetics

Following a single 9-hour application of XELSTRYM in pediatric patients 6 to 12 years with ADHD, the Cmax and AUC of dextroamphetamine were dose-proportional over the dose range of 4.5 mg/9 hours to 18 mg/9 hours.

After a single dose of 18 mg/9 hours of XELSTRYM or 70 mg of lisdexamfetamine in adults, the peak plasma concentration (Cmax) of dextroamphetamine were 44.6 ng/mL and 67.6 ng/mL, respectively; and area under concentration curve (AUCinf) of dextroamphetamine were 996 ng*h/mL and 1260 ng*h/mL, respectively. Median time-to-peak concentrations (tmax) was 9 hours for XELSTRYM and 4 hours for lisdexamfetamine.

The plasma PK profiles of dextroamphetamine following administration of XELSTRYM and lisdexamfetamine are shown in Figure 2.

Figure 2: Mean Plasma Concentrations versus Time Profile of Dextroamphetamine After a Single Dose Administration of XELSTRYM and Lisdexamfetamine in Healthy Adults

After multiple dosing of 18 mg/9 hours of XELSTRYM with application site rotation in adults or 70 mg of lisdexamfetamine (simulated), Cmax of dextroamphetamine were 68.8 ng/mL and 84.5 ng/mL, respectively; AUC0-24 of dextroamphetamine were 1150 ng*h/mL and 1248 ng*h/mL, respectively.

Absorption

The amount of dextroamphetamine absorbed systemically is a function of both wear time and transdermal system size. Peak plasma levels of dextroamphetamine were typically reached at 6 to 9 hours after single application and 6 hours after repeat applications of XELSTRYM when worn up to 9 hours.

On average, approximately 90% of dextroamphetamine is delivered from the transdermal system over 9 hours. Inter-individual variability for XELSTRYM as coefficient of variation (%CV) for the dextroamphetamine Cmax and AUC was generally about 20% to 30%.

After repeat applications of XELSTRYM for 4 weeks in adults with ADHD, there was 46% increase in Cmax and 54% increase in AUC0-24 when applied with rotating application sites for each transdermal system. There was 86% increase in Cmax and 104% increase in AUC0-24 when XELSTRYM was applied on the same site for 28 days.

Application of a heating pad on XELSTRYM for 6 consecutive hours led to a faster absorption rate (median Tmax about 6.5 hours) as compared with XELSTRYM without a heating pad (median Tmax about 8.5 hours). Geometric least square mean ratios for dextroamphetamine exposure, calculated as Cmax and AUC0-9h, were about 116% and 150%, respectively, compared with XELSTRYM without a heating pad, indicating the apparent heat effect on dextroamphetamine absorption.

The application of XELSTYRM to different sites (hip, upper arm, chest, upper back and flank) did not alter dextroamphetamine PK.

Elimination

When XELSTRYM is removed after 9 hours wear time, the mean apparent elimination half-life of dextroamphetamine ranged from 6.4 to 11.5 hours in the pediatric and adult population, respectively.

Metabolism

Amphetamine is reported to be oxidized at the 4 position of the benzene ring to form 4-hydroxyamphetamine, or on the side chain α or β carbons to form alpha-hydroxy-amphetamine or norephedrine, respectively. Norephedrine and 4-hydroxy-amphetamine are both active and each is subsequently oxidized to form 4-hydroxy-norephedrine. Alpha-hydroxy-amphetamine undergoes deamination to form phenylacetone, which ultimately forms benzoic acid and its glucuronide and the glycine conjugate hippuric acid. Although the enzymes involved in amphetamine metabolism have not been clearly defined, CYP2D6 is known to be involved with formation of 4-hydroxy-amphetamine. Since CYP2D6 is genetically polymorphic, population variations in amphetamine metabolism are a possibility.

Excretion

With normal urine pHs, approximately half of an administered oral dose of amphetamine is recoverable in urine as derivatives of alpha-hydroxy-amphetamine and approximately another 30-40% of the dose is recoverable in urine as amphetamine itself. Since amphetamine has a pKa of 9.9, urinary recovery of amphetamine is highly dependent on pH and urine flow rates. Alkaline urine pHs result in less ionization and reduced renal elimination, and acidic pHs and high flow rates result in increased renal elimination with clearances greater than glomerular filtration rates, indicating the involvement of active secretion. Urinary recovery of amphetamine has been reported to range from 1% to 75%, depending on urinary pH, with the remaining fraction of the dose hepatically metabolized. Consequently, both hepatic and renal dysfunction have the potential to inhibit the elimination of amphetamine and result in prolonged exposures. In addition, drugs that affect urinary pH are known to alter the elimination of amphetamine, and any decrease in amphetamine's metabolism that might occur due to drug interactions or genetic polymorphisms is more likely to be clinically significant when renal elimination is decreased [see DRUG INTERACTIONS (7)].

Specific Populations

The shapes of pharmacokinetic profiles after XELSTRYM application were generally similar between the pediatric and the adult population. Based on population PK, the median Cmax in pediatric patients 6 to 17 years are predicted to be 120% and 180%, respectively, the median AUC in pediatric patients are predicted to be 112% and 148%, respectively, of those in adults with a dose of 18 mg/9 hours.

Exposures of dextroamphetamine in specific populations evaluated with lisdexamfetamine are summarized in Figure 3.

Figure 3: Dextroamphetamine Exposures in Specific Populations

*Figure 3 shows the geometric mean ratios and the 90% confidence limits for Cmax and AUC of dextroamphetamine. Comparison for gender uses males as the reference. Comparison for age uses 55-64 years as the reference

Drug Interaction Studies

Effects of other drugs on the exposures of dextroamphetamine evaluated with lisdexamfetamine are summarized in Figure 4.

Figure 4: Effect of Other Drugs on Dextroamphetamine

The effects of dextroamphetamine on the exposures of other drugs evaluated with lisdexamfetamine are summarized in Figure 5.

Figure 5: Effects of Dextroamphetamine on Other Drugs

13 NONCLINICAL TOXICOLOGY

13.1 Carcinogenesis, Mutagenesis, Impairment of Fertility

Carcinogenesis

No evidence of carcinogenicity was found in studies in which d,l-amphetamine (enantiomer ratio of 1:1) was administered to mice and rats in the diet for 2 years at doses of up to 30 mg/kg/day in male mice, 19 mg/kg/day in female mice, and 5 mg/kg/day in male and female rats. Dermal carcinogenicity studies with dextroamphetamine were not conducted.

Mutagenesis

Amphetamine, in the enantiomer ratio d- to l- ratio of 3:1, was not clastogenic in the mouse bone marrow micronucleus test in vivo and was negative when tested in the E. coli component of the Ames test in vitro. d,l-Amphetamine (1:1 enantiomer ratio) has been reported to produce a positive response in the mouse bone marrow micronucleus test, an equivocal response in the Ames test, and negative responses in the in vitro sister chromatid exchange and chromosomal aberration assays.

Impairment of Fertility

Amphetamine, in the enantiomer ratio d- to l- ratio of 3:1, did not adversely affect fertility or early embryonic development in the rat at doses of up to 20 mg/kg/day.

13.2 Animal Toxicology and/or Pharmacology

Acute administration of high doses of amphetamine (d- or d,l-) has been shown to produce long-lasting neurotoxic effects, including irreversible nerve fiber damage, in rodents. The significance of these findings to humans is unknown.

14 CLINICAL STUDIES

The efficacy of XELSTRYM for the treatment of ADHD in adults and pediatric patients 6 to 17 years was established in a study with XELSTRYM in pediatric patients (presented below) and also based on adequate and well-controlled studies of lisdexamfetamine in pediatric and adult patients. Efficacy of lisdexamfetamine in the treatment of ADHD has been established in three short-term trials in pediatric patients 6 to 12 years, one short-term trial in pediatric patients 13 to 17 years, one short-term trial in pediatric patients 6 to 17 years, two short-term trials in adults 18 to 55 years, and two randomized withdrawal trials in pediatric patients 6 to 17 years and adults 18 to 55 years.

Pediatric Patients 6 to 17 years with ADHD

The efficacy of XELSTRYM for the treatment of ADHD in pediatric patients 6 to 17 years was evaluated in a multi-center, randomized, double-blind, placebo-controlled, cross-over design, modified analog classroom study (Study 1; NCT01711021). The study was conducted in 110 patients who met DSM-IV-TR criteria for ADHD.

Following a 5-week open-label, dose optimization phase with XELSTRYM (4.5 mg/9 hours, 9 mg/9 hours, 13.5 mg/9 hours and 18 mg/9 hours), patients were randomized to one of two treatment sequences: 1) XELSTRYM (optimized dose) followed by placebo, each for one week, or 2) placebo followed by XELSTRYM (optimized dose), each for one week. Efficacy was assessed at the end of each week using the Swanson, Kotkin, Agler, M.Flynn, and Pelham (SKAMP) total score, a validated 13-item rating scale to assess manifestations of ADHD in a classroom setting. Items are specific to place (classroom setting) and time (during a typical classroom period), and the scale is used to assess multiple ratings taken within a day.

Efficacy was solely based on data from Period 1, which was the first week of the two-week double-blind, placebo-controlled, crossover treatment phase. A statistically significant separation from placebo was observed with use of XELSTRYM in Period 1 (Table 5). Changes in SKAMP total scores assessed at pre-dose (-0.5 hours) and at 1, 2, 3, 4.5, 6, 7, 9, 10, and 12 hours post-application are presented in Figure 6.

Table 5: Summary of Primary Efficacy Results: SKAMP Total Score Averaged Over Classroom Day in Pediatric Patients (6 to 17 years) with ADHD (Period 1 Data only)

Study Number | Treatment Group | Pre-Dose Score on Classroom Dayb Mean (SD) | LS Meanc (SE) | Placebo-subtracted Differenced (95% CI)
Study 1 | XELSTRYMa | 13.6 (5.9) | 12.4 (1.2) | -4.7 (-8.0, -1.4)
Study 1 | Placebo | 12.7 (7.9) | 17.1 (1.2) | --------
SD: standard deviation; SE: standard error; LS Mean: least-squares mean; CI: confidence interval.
a Statistically significant to placebo.
b Pre-dose score on Period 1 classroom day.
c LS mean over hours 1, 2, 3, 4.5, 6, 7, 9, 10, and 12 hours post-dose on Period 1 classroom day.
d Difference (drug minus placebo) in least-squares means on Period 1 classroom day.

Figure 6: LS Mean SKAMP Total Score After Treatment with XELSTRYM or Placebo in Period 1 Classroom Day in Pediatric Patients (6 to 17 years) with ADHD (Study 1)

Adhesion

Based on a clinical study in adult subjects wearing XELSTRYM 18 mg/9 hours, 233 of 238 transdermal systems (98%) exhibited 75% or greater surface area adhesion at all timepoints evaluated (every hour) throughout the 9-hour wear period. In another study in which pediatric patients 6 to 17 years and adult patients wearing XELSTRYM 4.5 mg/9 hours or 18 mg/9 hours were not confined to the clinical unit, 50 out of 58 transdermal systems (86%) exhibited 75% or greater surface area adhesion at 9 hours; 3 transdermal systems (5%) were reported as fully detached during the study.

16 HOW SUPPLIED/STORAGE AND HANDLING

How Supplied

XELSTRYM (dextroamphetamine) transdermal system is a translucent product with a printed backing on one side and a release liner on the other packaged in an individual pouch supplied as:

- 4.5 mg/9 hours transdermal system (system size: 4.76 cm^2)
  Carton of 30 transdermal systems, each transdermal system is packaged in an individual pouch
  NDC 68968-0205-3

- 9 mg/9 hours transdermal system (system size: 9.52 cm^2)
  Carton of 30 transdermal systems, each transdermal system is packaged in an individual pouch
  NDC 68968-0210-3

- 13.5 mg/9 hours transdermal system (system size: 14.29 cm^2)
  Carton of 30 transdermal systems, each transdermal system is packaged in an individual pouch
  NDC 68968-0215-3

- 18 mg/9 hours transdermal system (system size: 19.05 cm^2)
  Carton of 30 transdermal systems, each transdermal system is packaged in an individual pouch
  NDC 68968-0220-3

Storage and Handling

Store at 68°F to 77° F (20°C to 25° C); excursions permitted between 15°C to 30° C (59 to 86° F) [see USP Controlled Room Temperature]. Protect from light.

Store XELSTRYM in the individual sealed pouch until use. Apply immediately upon removal from the protective pouch.

17 PATIENT COUNSELING INFORMATION

Advise the patient to read the FDA-approved patient labeling (Medication Guide and Instructions for Use).

Abuse, Misuse, and Addiction

Educate patients and their families about the risks of abuse, misuse, and addiction of XELSTRYM, which can lead to overdose and death, and proper disposal of any unused drug [see WARNINGS AND PRECAUTIONS (5.1), DRUG ABUSE AND DEPENDENCE (9.2), OVERDOSAGE (10)]. Advise patients to store XELSTRYM in a safe place, preferably locked, and instruct patients to not give XELSTRYM to anyone else.

Risks to Patients with Serious Cardiac Disease

Advise patients that there are potential risks to patients with serious cardiac disease, including sudden death, with XELSTRYM use. Instruct patients to contact a healthcare provider immediately if they develop symptoms such as exertional chest pain, unexplained syncope, or other symptoms suggestive of cardiac disease [see WARNINGS AND PRECAUTIONS (5.2)].

Increased Blood Pressure and Heart Rate

Advise patients that XELSTRYM can elevate blood pressure and heart rate [see WARNINGS AND PRECAUTIONS (5.3)].

Psychiatric Adverse Reactions

Advise patients that XELSTRYM, at recommended doses, can cause psychotic or manic symptoms, even in patients without prior history of psychotic symptoms or mania [see WARNINGS AND PRECAUTIONS (5.4)].

Long-Term Suppression of Growth in Pediatric Patients

Advise patients that XELSTRYM may cause slowing of growth including weight loss [see WARNINGS AND PRECAUTIONS (5.5)].

Circulation problems in fingers and toes [Peripheral vasculopathy, including Raynaud's phenomenon]

Instruct patients beginning treatment with XELSTRYM about the risk of peripheral vasculopathy, including Raynaud's Phenomenon, and associated signs and symptoms: fingers or toes may feel numb, cool, painful, and/or may change from pale, to blue, to red. Instruct patients to report to their physician any new numbness, pain, skin color change, or sensitivity to temperature in fingers or toes. Instruct patients to call their physician immediately with any signs of unexplained wounds appearing on fingers or toes while taking XELSTRYM. Further clinical evaluation (e.g. rheumatology referral) may be appropriate for certain patients [see WARNINGS AND PRECAUTIONS (5.6)].

Serotonin Syndrome

Caution patients about the risk of serotonin syndrome with concomitant use of XELSTRYM and other serotonergic drugs including SSRIs, SNRIs, triptans, tricyclic antidepressants, fentanyl, lithium, tramadol, tryptophan, buspirone, St. John's Wort, and with drugs that impair metabolism of serotonin (in particular MAOIs, both those intended to treat psychiatric disorders and also others such as linezolid [see CONTRAINDICATIONS (4), WARNINGS AND PRECAUTIONS (5.7) and DRUG INTERACTIONS (7.1)]. Advise patients to contact their healthcare provider or report to the emergency room if they experience signs or symptoms of serotonin syndrome.

Application Site Reactions

Inform patients that application site reactions, including pain, pruritus, burning sensation, erythema, discomfort, edema, or swelling have been reported with the use of XELSTRYM. Inform patients that increased skin irritation, discomfort or pain may occur if the same application site is used repeatedly. Instruct patients to select a different application site each day to minimize skin reactions. Patients should monitor for these reactions while wearing or immediately after removal of XELSTRYM. Discontinue XELSTRYM if contact sensitization is suspected [see WARNINGS AND PRECAUTIONS (5.9)].

External Heat

Inform patients to avoid exposing XELSTRYM to external heat sources, such as hair dryers, heating pads, electric blankets, heated water beds, etc. [see WARNINGS AND PRECAUTIONS (5.10)].

Motor and Verbal Tics, and Worsening of Tourette’s Syndrome

Advise patients that motor and verbal tics and worsening of Tourette’s Syndrome may occur during treatment with XELSTRYM. Instruct patients to notify their healthcare provider if emergence of new tics or worsening of tics or Tourette’s syndrome occurs [see WARNINGS AND PRECAUTIONS (5.11)].

Concomitant Medications

Advise patients to notify their physicians if they are taking, or plan to take, any prescription or over-the-counter drugs because there is a potential for interactions [see DRUG INTERACTIONS (7.1)].

Pregnancy Registry

Advise patients that there is a pregnancy exposure registry that monitors pregnancy outcomes in women exposed to XELSTRYM during pregnancy [see USE IN SPECIFIC POPULATIONS (8.1)].

Pregnancy

Advise patients of the potential fetal effects from the use of XELSTRYM during pregnancy. Advise patients to notify their healthcare provider if they become pregnant or intend to become pregnant during treatment with XELSTRYM [see USE IN SPECIFIC POPULATIONS (8.1)].

Lactation

Advise women not to breastfeed if they are taking XELSTRYM [see USE IN SPECIFIC POPULATIONS (8.2)].

Impairment in Ability to Operate Machinery or Vehicles

XELSTRYM may impair the ability of the patient to engage in potentially hazardous activities such as operating machinery or vehicles. Instruct patients to find out how XELSTRYM will affect them before engaging in potentially hazardous activities [see ADVERSE REACTIONS (6.1, 6.2)].

Administration Instructions

Inform patients/caregivers:

- to apply one XELSTRYM transdermal system at a time for not more than 9 hours and use only one XELSTRYM per 24 hours.
- of the application sites: hip, upper arm, chest, upper back, or flank. Advise them to select a different application site each time a new XELSTRYM transdermal system is applied.
- to apply XELSTRYM to clean, dry, and intact skin.
- to wash their hands immediately if they touch the adhesive side of the transdermal system to avoid amphetamine absorption and to check XELSTRYM periodically throughout the wear time [see DOSAGE AND ADMINISTRATION (2.3)].

Manufactured by: Noven Pharmaceuticals, Inc., Miami, FL 33186
For more information, go to www.xelstrym.com or call 1-800-455-8070.
Xelstrym® is a registered trademark of Noven Therapeutics, LLC.
© 2025 Noven Pharmaceuticals, Inc.
102668-3

Medication Guide

XELSTRYM® (Zel’ Strim)
(dextroamphetamine)
transdermal system, CII

What is the most important information I should know about XELSTRYM?

XELSTRYM may cause serious side effects, including:

- Abuse, misuse, and addiction. XELSTRYM has a high chance for abuse and misuse and may lead to substance use problems, including addiction. Misuse and abuse of XELSTRYM, other amphetamine containing medicines, and methylphenidate containing medicines, can lead to overdose and death. The risk of overdose and death is increased with higher doses of XELSTRYM or when it is used in ways that are not approved, such as snorting or injection.
  - Your healthcare provider should check you or your child’s risk for abuse, misuse, and addiction before starting treatment with XELSTRYM and will monitor you or your child during treatment.
  - XELSTRYM may lead to physical dependence after prolonged use, even if taken as directed by your healthcare provider.
  - Do not give XELSTRYM to anyone else. See “What is XELSTRYM?” for more information.
  - Keep XELSTRYM in a safe place and properly dispose of any unused medicine. See “How should I store XELSTRYM?” for more information.
  - Tell your healthcare provider if you or your child have ever abused or been dependent on alcohol, prescription medicines, or street drugs.
- Risks for people with serious heart disease. Sudden death has happened in people who have heart defects or other serious heart disease.
  Your healthcare provider should check you or your child carefully for heart problems before starting treatment with XELSTRYM. Tell your healthcare provider if you or your child have any heart problems, heart disease, or heart defects.
  Call your healthcare provider or go to the nearest hospital emergency room right away if you or your child have any signs of heart problems such as chest pain, shortness of breath, or fainting during treatment with XELSTRYM.
- Increased blood pressure and heart rate.
  Your healthcare provider should check your or your child’s blood pressure and heart rate regularly during treatment with XELSTRYM.

- Mental (psychiatric) problems, including:
  - new or worse behavior and thought problems
  - new or worse bipolar illness
  - new psychotic symptoms (such as hearing voices, or seeing or believing things that are not real) or new manic symptoms
  Tell your healthcare provider about any mental problems you or your child have or about a family history of suicide, bipolar illness, or depression.
  Call your healthcare provider right away if you or your child have any new or worsening mental symptoms or problems during treatment with XELSTRYM, especially hearing voices, seeing or believing things that are not real, or new manic symptoms.

What is XELSTRYM?

XELSTRYM is a central nervous system (CNS) stimulant prescription medicine used for the treatment of Attention-Deficit Hyperactivity Disorder (ADHD) in adults and children 6 years of age and older. XELSTRYM may help increase attention and decrease impulsiveness and hyperactivity in adults and children 6 years of age and older with ADHD.

XELSTRYM is not recommended for use in children under 6 years of age with ADHD.

XELSTRYM is a federally controlled substance (CII) because it contains dextroamphetamine that can be a target for people who abuse prescription medicines or street drugs. Keep XELSTRYM in a safe place to protect it from theft. Never give your XELSTRYM to anyone else, because it may cause death or harm them. Selling or giving away XELSTRYM may harm others and is against the law.

Do not use XELSTRYM if you or your child are:

- allergic to amphetamine products or any of the ingredients in XELSTRYM. See the end of the Medication Guide for a complete list of ingredients in XELSTRYM.
- taking or have taken within the past 14 days a medicine called a monoamine oxidase inhibitor (MAOI), including the antibiotic linezolid or the intravenous medicine called methylene blue.

Before using XELSTRYM, tell your healthcare provider about all medical conditions, including if you or your child:

- have heart problems, heart disease, heart defects, or high blood pressure
- have mental problems including psychosis, mania, bipolar illness, or depression or have a family history of suicide, bipolar illness, or depression
- have circulation problems in fingers and toes
- have kidney problems. Your healthcare provider may lower your dose.
- have or had repeated movements or sounds (tics) or Tourette's syndrome, or have a family history of tics or Tourette's syndrome
- are pregnant or plan to become pregnant. It is not known if XELSTRYM will harm the unborn baby.
  - There is a pregnancy registry for women who are exposed to XELSTRYM during pregnancy. The purpose of the registry is to collect information about the health of women exposed to XELSTRYM and their babies. If you or your child becomes pregnant during treatment with XELSTRYM, talk to your healthcare provider about registering with the National Pregnancy Registry for Psychiatric Medications at 1-866-961-2388 or visit online at https://womensmentalhealth.org/clinical-and-research-programs/pregnancyregistry/othermedications/.
- are breastfeeding or plan to breastfeed. XELSTRYM passes into breast milk. You or your child should not breastfeed during treatment with XELSTRYM. Talk to your healthcare provider about the best way to feed the baby during treatment with XELSTRYM.

Tell your healthcare provider about all the medicines that you or your child take, including prescription and over-the-counter medicines, vitamins, and herbal supplements.

XELSTRYM may affect the way other medicines work and other medicines may affect how XELSTRYM works. Using XELSTRYM with other medicines may cause serious side effects. Sometimes the doses of other medicines will need to be changed while using XELSTRYM.

Especially tell your healthcare provider if you or your child take:

- selective serotonin reuptake inhibitors (SSRIs)
- medicines used to treat migraine headaches called triptans
- lithium
- tramadol
- buspirone

- serotonin norepinephrine reuptake inhibitors (SNRIs)
- tricyclic antidepressants
- fentanyl
- tryptophan
- St. John’s Wort

Your healthcare provider will decide whether XELSTRYM can be used with other medicines. Do not start any new medicine during treatment with XELSTRYM without first talking to your healthcare provider.

How should XELSTRYM be used?

- See the detailed “Instructions for Use” at the end of this XELSTRYM Medication Guide for information about the right way to apply, remove, and dispose of XELSTRYM.
- Your healthcare provider may change the dose if needed.
- Apply 1 XELSTRYM patch at a time for not more than 9 hours. Use only 1 XELSTRYM per 24 hours and change the site of application when applying a new patch.
- Apply the XELSTRYM patch 2 hours before the effect is needed and remove XELSTRYM within 9 hours after application.

If you or your child use too much XELSTRYM, call your healthcare provider or Poison Help line at 1-800-222-1222 or go to the nearest hospital emergency room right away.

What should I avoid while using XELSTRYM?

- Do not drive, operate heavy machinery, or do other potentially dangerous activities until you know how XELSTRYM affects you.
- After applying the XELSTRYM patch, avoid exposing the application site to direct external heat sources, such as hair dryers, heating pads or electric blankets, heat lamps, saunas, hot tubs, and heated water beds. Exposure to heat can cause too much medicine to pass into your body and cause serious side effects.

What are possible side effects of XELSTRYM?

XELSTRYM may cause serious side effects, including:

- See “What is the most important information I should know about XELSTRYM”
- Slowing of growth (weight and height) in children. Children should have their height and weight checked often during treatment with XELSTRYM. Your healthcare provider may stop the treatment with XELSTRYM if your child is not growing or gaining height or weight as expected.
- Circulation problems in fingers and toes (peripheral vasculopathy, including Raynaud's phenomenon):
  - fingers or toes may feel numb, cool, painful
  - fingers or toes may change color from pale, to blue, to red
  Tell your healthcare provider if you or your child have numbness, pain, skin color change, or sensitivity to temperature in your fingers or toes.
  Call your healthcare provider right away if you or your child have any signs of unexplained wounds appearing on fingers or toes during treatment with XELSTRYM.
- Serotonin Syndrome. A potentially life-threatening problem called serotonin syndrome may happen when XELSTRYM is used with certain other medicines. See “Before using XELSTRYM, tell your healthcare provider about all medical conditions, including if you or your child:” Stop using XELSTRYM and call your healthcare provider or go to the nearest hospital emergency room right away if you or your child develop any of the following signs and symptoms of serotonin syndrome:

- agitation
- fast heartbeat
- flushing
- seizures
- coma
- sweating
- loss of coordination

- confusion
- dizziness
- tremors, stiff muscles, or muscle twitching
- seeing or hearing things that are not real (hallucination)
- changes in blood pressure
- high body temperature (hyperthermia)
- nausea, vomiting, diarrhea

- Allergic skin rash (contact sensitization). Stop using XELSTRYM and tell your healthcare provider right away if you or your child develop swelling or blisters at or around the application site. You may have a skin allergy to XELSTRYM. People who have skin allergies to XELSTRYM may develop an allergy to all amphetamine containing products, even amphetamine products that are taken by mouth.
- Application site reactions have happened with XELSTRYM while wearing the XELSTRYM patch, and after removal of the patch. Signs and symptoms of an application site reaction include, pain, Itching, burning feeling, redness, discomfort, or swelling at the application site. Call your healthcare provider if you or your child develop any application site reactions that do not resolve on their own.
- New or worsening tics or worsening Tourette’s syndrome. Tell your healthcare provider if you or your child get any new or worsening tics or worsening Tourette’s syndrome during treatment with XELSTRYM.

The most common side effects of XELSTRYM include:

- decreased appetite
- trouble sleeping
- stomach pain
- nausea
- increased blood pressure

- headache
- muscle twitching (tics)
- vomiting
- irritability
- increased heart rate

These are not all the possible side effects of XELSTRYM.

Call your doctor for medical advice about side effects. You may report side effects to FDA at 1-800-FDA-1088.

How should I store XELSTRYM?

- Store XELSTRYM at room temperature between 68°F to 77℉F (20℃ to 25℃).
- Store XELSTRYM in a safe place, like a locked cabinet.
- Protect XELSTRYM from light and moisture.
- Keep XELSTRYM in their unopened pouches until you are ready to use them.
- Dispose of remaining unused or expired XELSTRYM by a medication take-back program at a U.S. Drug Enforcement Administration (DEA) authorized collection site. If no take-back program or DEA authorized collector is available, each unused patch should be removed from its individual pouch, separated from the protective liner, folded in half so the sticky sides stick together, and thrown away in a container with a lid in the household trash. Do not flush the XELSTRYM patch, pouch, or liner down the toilet. Visit www.fda.gov/drugdisposal for additional information on disposal of unused medicines.

Keep XELSTRYM and all medicines out of the reach of children.

General information about the safe and effective use of XELSTRYM.

Medicines are sometimes prescribed for purposes other than those listed in a Medication Guide. Do not use XELSTRYM for a condition for which it was not prescribed. Do not give XELSTRYM to other people, even if they have the same symptoms that you have. It may harm them and it is against the law. You can ask your healthcare provider or pharmacist for information about XELSTRYM that is written for healthcare professionals.

What are the ingredients in XELSTRYM?

Active ingredient: dextroamphetamine

Inactive ingredients: acrylic adhesives, green ink, polyester/polyurethane backing, and polyester release liner

Manufactured by: Noven Pharmaceuticals, Inc., Miami, FL 33186

Xelstrym® is a registered trademark of Noven Therapeutics, LLC.

For more information, go to www.xelstrym.com or call 1-800-455-8070.

This Medication Guide has been approved by the U.S. Food and Drug Administration.

Revised: 9/2025

102668-3

INSTRUCTIONS FOR USE

XELSTRYM® (Zel’ Strim)
(dextroamphetamine)
transdermal system, CII

This Instructions for Use contains information on how to apply, remove, and dispose of XELSTRYM transdermal system (patch).

XELSTRYM transdermal system (patch) is for use on skin only.

Read this Instructions for Use before you start using XELSTRYM and each time you get a refill. There may be new information. This information does not take the place of talking to your healthcare provider about your or your child’s medical condition or treatment.

XELSTRYM is supplied in cartons containing 30 patches. Each patch is sealed in a pouch protecting it until you are ready to apply it.

Important information you need to know before applying XELSTRYM:

- Wear only 1 patch at a time.
- A new patch must be applied every day.
- Do not wear XELSTRYM for more than 9 hours. Use only 1 patch per day (per 24 hours).
- When you apply a new patch, choose a different application site from the one used the previous day to reduce the chance of skin reactions such as irritation, discomfort or pain at the application site.
- Avoid touching the sticky side of XELSTRYM with your fingers. If you accidentally touch the sticky side of the patch, wash your hands right away with soap and water to remove any potential medicine that may have stuck to your fingers. Do not use hand sanitizer in place of soap and water.
- Avoid exposing the application site to direct external heat sources, such as heating pads or electric blankets, heat lamps, saunas, hot tubs, heated water beds, and hair dryers.
- Check to see if the patch has become loose after bathing, showering or swimming.
- If the patch falls off:
  - Do not reapply the same patch. Fold the patch in half so that the sticky sides are together and throw away the patch as instructed below in Steps 5 to 7.
  - You should choose a different application site and apply a new patch.
  - The total wear time for the first patch that fell off and the second replacement patch should not total more than 9 hours in 1 day (24 hours).
  - Parents or caregivers of children prescribed XELSTRYM should instruct the child to tell an adult if the patch becomes loose or falls off.

Figure A (not to scale).

Applying XELSTRYM:

Step 1: Select the patch application site (see Figure B).

- Choose 1 application site, on either the left or right side, to apply 1 patch. The recommended application sites include:
  - chest
  - upper arm
  - upper back
  - flank (sides of the waist)
  - hip
- Do not apply a patch to any other site.
- Avoid areas of tight clothing, such as waistbands or straps.
- Choose a different application site from the one used the previous day when you apply a new patch.
- Check the expiration date before applying the patch.

Figure B

Step 2: Check the skin where XELSTRYM will be applied. Make sure it is:

- Not damaged (cut, scraped, burned), irritated (rashes), or has any other skin problems
- Cleaned with soap and water (not an alcohol-based product), dry (not wet), with no powder, oil, lotion, or gel
- Hairless or nearly hairless. Applying the patch to a hairy application site could result in the patch falling off

If there is hair at the patch application site, do not shave the application site. Use scissors to clip hair as close to the skin as possible.

Step 3: Applying XELSTRYM

- Do not open the pouch until you are ready to apply the patch.
- Using scissors, carefully cut along the right side of the pouch. Start at the dashed line marked on the pouch as “Step 1. Cut This Side” and cut along the entire length of the pouch, through the bar code (see Figure C).
- Next, carefully cut the top of the pouch along the dashed line marked on the pouch as “Step 2. Cut Across Top” (see Figure D).
- Gently remove the contents of the pouch and throw away the slip liners (additional pieces of clear plastic) above and below the patch (see Figure A, Figure E).
  - Do not use the patch if it is cut or damaged
  - Apply the patch right away after removing it from the pouch

Figure C

Figure D

Figure E

- Gently peel away half of the clear plastic liner. Avoid touching the sticky side with your fingers (see Figure F).
- Apply the sticky side of the patch to the application site you selected and smooth it down (see Figure G).

Figure F

Figure G

- Hold the edge of the remaining protective liner, slowly peel it off and smooth the patch down (see Figure H).
- Press the patch firmly with the palm of your hand (See Figure I).
  - Smooth the patch to make sure it sticks well to your skin.

XELSTRYM patch should not be applied or reapplied with dressings, tape, or other adhesives.

Figure H

Figure I

- Wash your hands with soap and water after applying the patch (see Figure J).
  Do not use hand sanitizer in place of soap and water.

Figure J

Step 4: Check XELSTRYM regularly during the day to make sure it is completely sticking to the application site. Also check the patch when:

- using the bathroom
- after sleeping
- after bathing, showering or swimming

- undressing or changing clothes
- if sweating a lot

- If patch edges lift, smooth the patch down on the skin and press firmly with the palm of your hand. XELSTRYM patch should not be reapplied with dressings, tape, or other adhesives.
- If the patch falls off, do not reapply the same patch. Fold the patch in half so that the sticky sides are together and throw away the patch as instructed below in Steps 5 to 7. You may apply a new patch to a different application site. The total wear time for the first patch that fell off and the second replacement patch should not be more than a total of 9 hours in 1 day (24 hours).
- Parents or caregivers of children prescribed XELSTRYM should instruct the child to tell an adult if the patch becomes loose or falls off.

XELSTRYM Application Schedule for 9 Hour Wear Time:

If you put the patch on at: | On the same day, remove the patch no later than:
6:00 a.m. | 3:00 p.m
7:00 a.m. | 4:00 p.m
8:00 a.m. | 5:00 p.m
9:00 a.m. | 6:00 p.m
10:00 a.m. | 7:00 p.m
11:00 a.m. | 8:00 p.m
12:00 p.m. | 9:00 p.m

Removing and Disposing Used XELSTRYM:

Step 5: After 9 hours, remove XELSTRYM and fold it in half so that the sticky sides stick together (see Figure K) to avoid accidental exposure to medicine.

- If any adhesive (glue) remains on your skin after you remove the patch, apply an oil-based product or water and soap to the skin to remove the glue.

Figure K

Step 6: Throw away the used patch in a container with a lid right away (see Figure L).

Figure L

Step 7: Wash your hands with soap and water after throwing the patch away (see Figure M).
Do not use hand sanitizer in place of soap and water.

Figure M

Storing XELSTRYM

- Store XELSTRYM at room temperature between 68°F to 77°F (20°C to 25°C).
- Store XELSTRYM in a safe place, like a locked cabinet.
- Protect XELSTRYM from light and moisture.
- Keep XELSTRYM in their unopened pouches until you are ready to use them.
- Keep XELSTRYM and all medicines out of the reach of children.

Disposing of Unused XELSTRYM:

Dispose of remaining unused or expired XELSTRYM by a medication take-back program at a U.S. Drug Enforcement Administration (DEA) authorized collection site. If no take-back program or DEA authorized collector is available, each unused patch should be removed from its individual pouch, separated from the protective liner, folded in half so the sticky sides stick together, and thrown away in a container with a lid in the household trash. Do not flush the XELSTRYM patch, pouch, or liner down the toilet. Visit www.fda.gov/drugdisposal for additional information on disposal of unused medicines.

This Instructions for Use has been approved by the U.S. Food and Drug Administration.
© 2023 Noven Pharmaceuticals, Inc.
102668-3

Revised: 10/2023